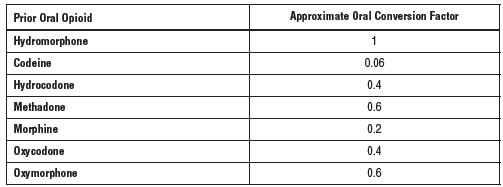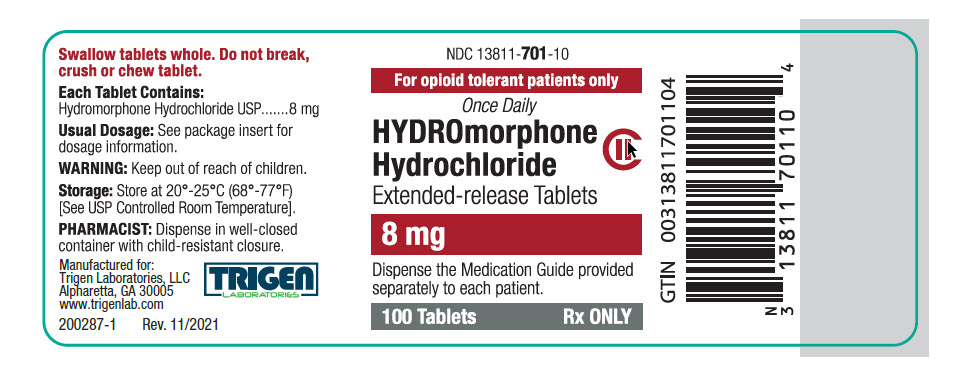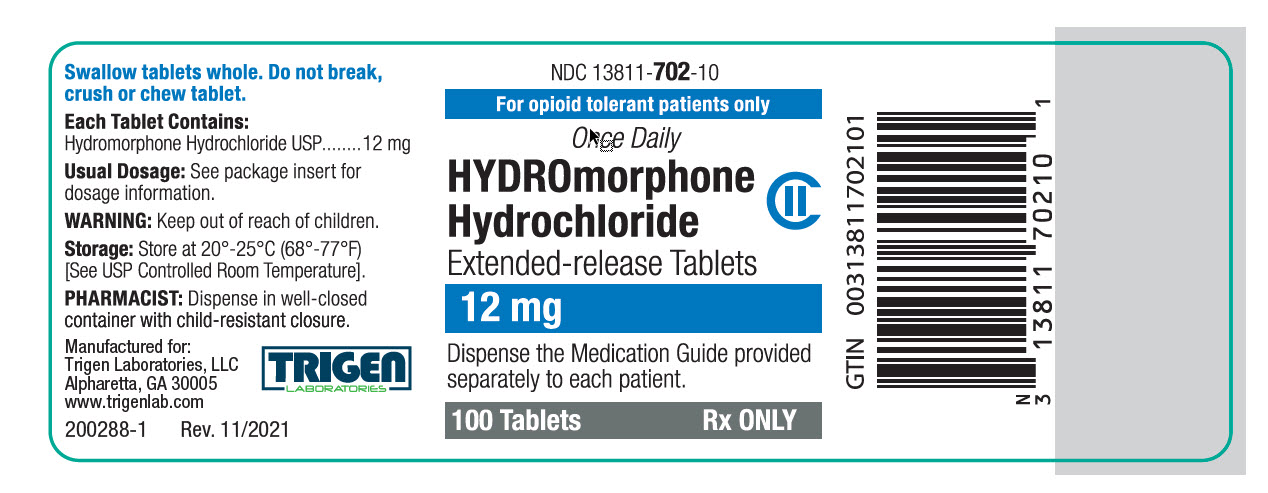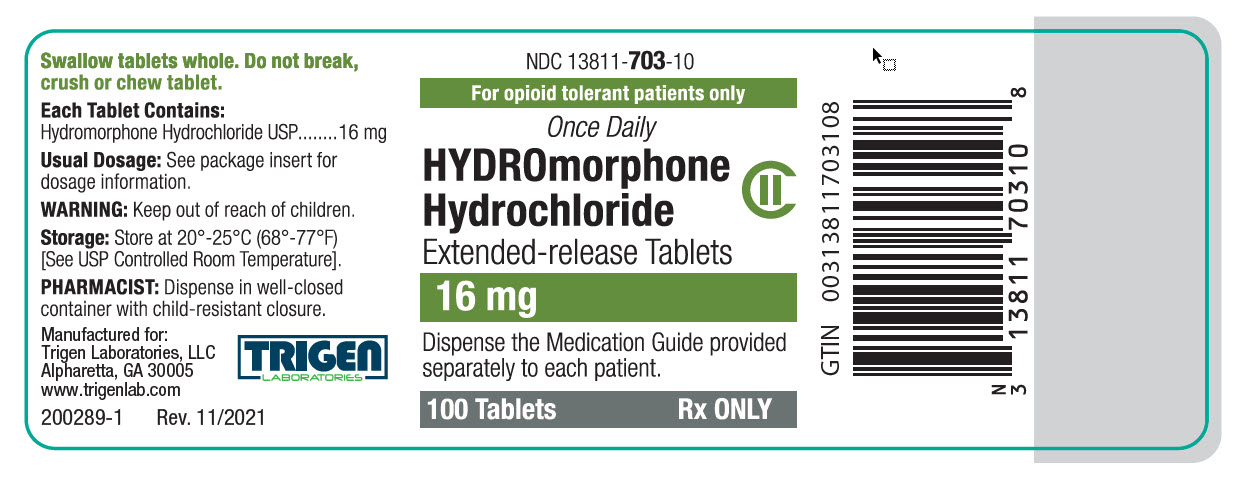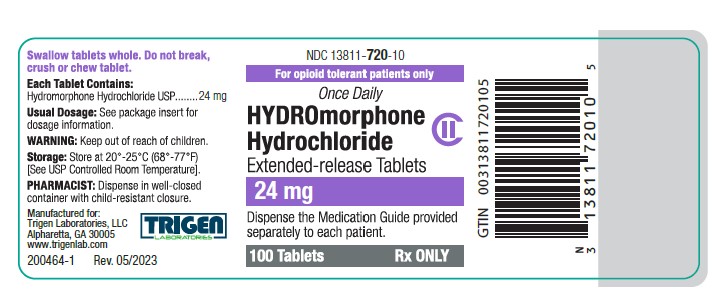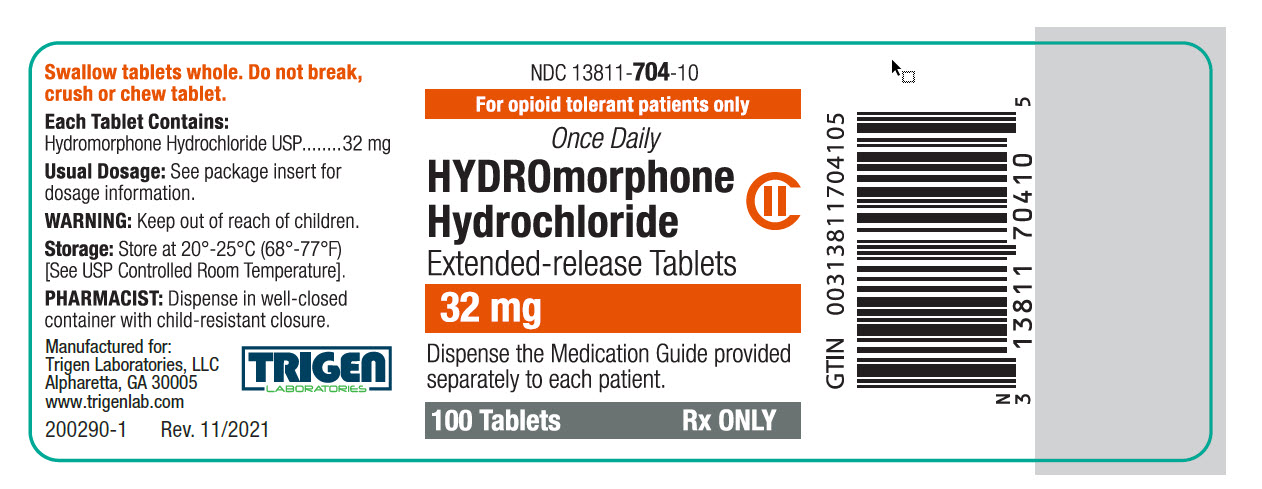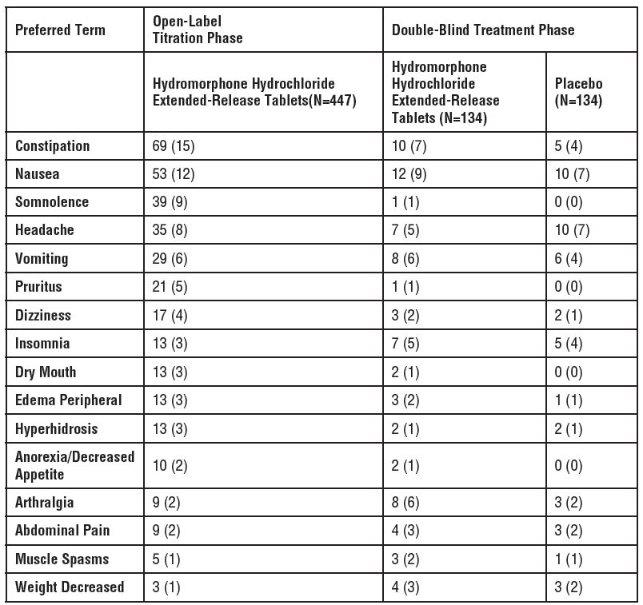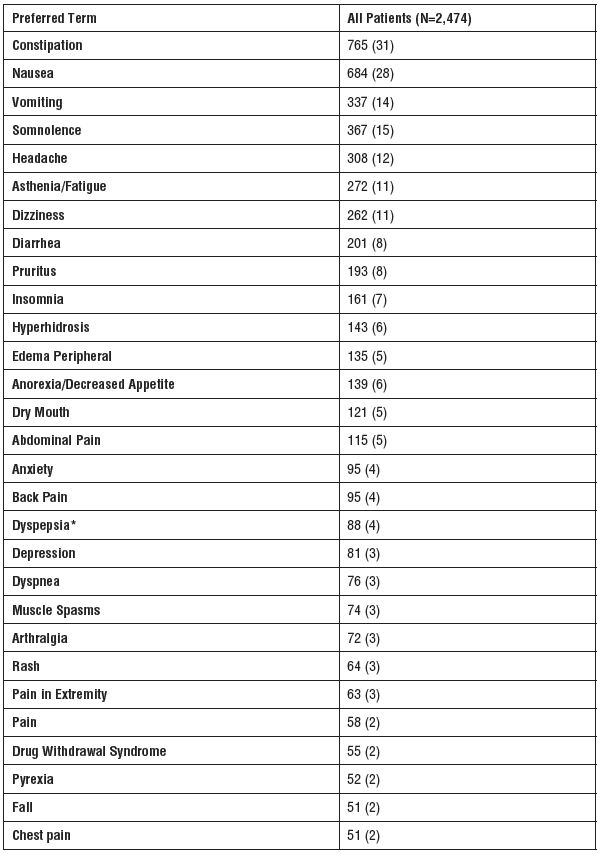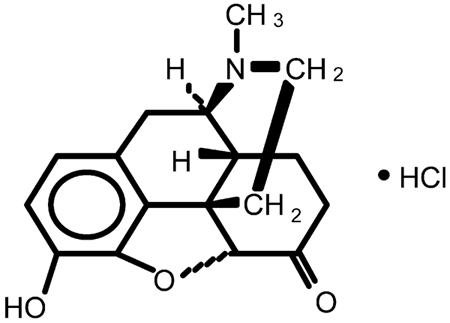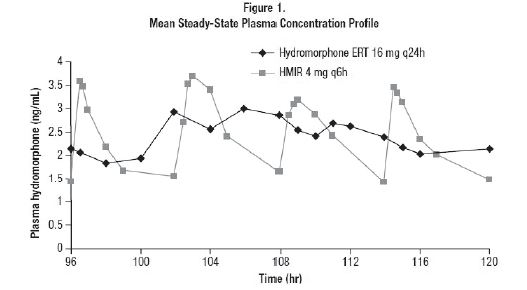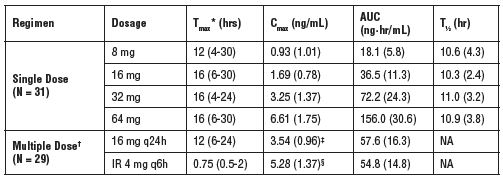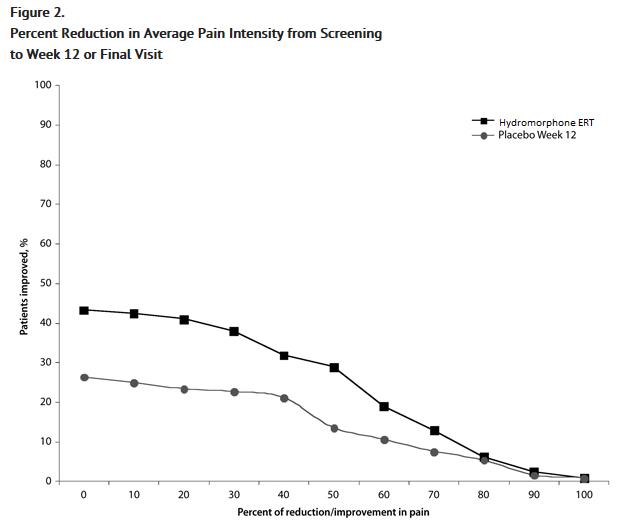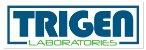 DRUG LABEL: Hydromorphone Hydrochloride
NDC: 13811-703 | Form: TABLET, EXTENDED RELEASE
Manufacturer: Trigen Laboratories, LLC
Category: prescription | Type: HUMAN PRESCRIPTION DRUG LABEL
Date: 20251225
DEA Schedule: CII

ACTIVE INGREDIENTS: HYDROMORPHONE HYDROCHLORIDE 16 mg/1 1
INACTIVE INGREDIENTS: CELLULOSE ACETATE; FERROSOFERRIC OXIDE; FERRIC OXIDE YELLOW; HYPROMELLOSE 2910 (5 MPA.S); LACTOSE MONOHYDRATE; MAGNESIUM STEARATE; POLYETHYLENE GLYCOL, UNSPECIFIED; SODIUM CHLORIDE; TITANIUM DIOXIDE; TRIACETIN; SILICON DIOXIDE; POLYETHYLENE OXIDE 200000; HYPROMELLOSE 2208 (100 MPA.S); D&C YELLOW NO. 10 ALUMINUM LAKE; FD&C YELLOW NO. 6 ALUMINUM LAKE; POLYETHYLENE GLYCOL 7000000

HIGHLIGHTS OF PRESCRIBING INFORMATION

These highlights do not include all the information needed to use HYDROMORPHONE HYDROCHLORIDE EXTENDED-RELEASE TABLETS safely and effectively. See full prescribing information for HYDROMORPHONE HYDROCHLORIDE EXTENDED-RELEASE TABLETS.
HYDROMORPHONE HYDROCHLORIDE extended-release tablets,
for oral use, CII
Initial U.S. Approval: 1984

WARNING: SERIOUS AND LIFE-THREATENING RISKS FROM USE OF HYDROMORPHONE HYDROCHLORIDE EXTENDED-RELEASE TABLETS

See full prescribing information for complete boxed warning.

- Hydromorphone hydrochloride extended-release tablets expose users to risks of addiction, abuse, and misuse, which can lead to overdose and death. Assess patient’s risk before prescribing, and reassess regularly for these behaviors and conditions. (5.1)
- Serious, life-threatening, or fatal respiratory depression may occur, especially upon initiation or following a dosage increase. To reduce the risk of respiratory depression, proper dosing and titration of hydromorphone hydrochloride extended-release tablets are essential. Instruct patients to swallow hydromorphone hydrochloride extended-release tablets whole to avoid exposure to a potentially fatal dose of hydromorphone. (5.2)
- Accidental ingestion of hydromorphone hydrochloride extended-release tablets, especially by children, can result in fatal overdose of hydromorphone. (5.4)
- Concomitant use of opioids with benzodiazepines or other central nervous system (CNS) depressants, including alcohol, may result in profound sedation, respiratory depression, coma, and death. Reserve concomitant prescribing for use in patients for whom alternative treatment options are inadequate. (5.3, 7)
- Advise pregnant women using opioids for an extended period of time of the risk of Neonatal Opioid Withdrawal Syndrome, which may be life-threatening if not recognized and treated. Ensure that management by neonatology experts will be available at delivery. (5.4)
- Healthcare providers are strongly encouraged to complete a REMS compliant education program and to counsel patients and caregivers on serious risks, safe use, and the importance of reading the Medication Guide with each prescription.

RECENT MAJOR CHANGES

Boxed Warning 12/2025

Indications and Usage (1) 12/2025

Dosage and Administration (2.2, 2.5) 12/2025

Warnings and Precautions (5.1, 5.2, 5.3, 5.11, 5.13) 12/2025

1 INDICATIONS AND USAGE

Hydromorphone hydrochloride extended-release tablets are an opioid agonist indicated in opioid-tolerant patients for the management of severe and persistent pain that requires an opioid analgesic and that cannot be adequately treated with alternative options, including immediate-release opioids.

Patients considered opioid tolerant are those who are taking, for one week or longer, at least 60 mg oral morphine per day, 25 mcg transdermal fentanyl per hour, 30 mg oral oxycodone per day, 8 mg oral hydromorphone per day, 25 mg oral oxymorphone per day, 60 mg oral hydrocodone per day, or an equianalgesic dose of another opioid (1).

Limitations of Use:

- Because of the risks of addiction, abuse, misuse, overdose, and death, which can occur at any dosage or duration and persist over the course of therapy, reserve opioid analgesics, including hydromorphone hydrochloride extended-release tablets for use in patients for whom alternative treatment options are ineffective, not tolerated, or would be otherwise inadequate to provide sufficient management of pain. (1, 5.1)
- Hydromorphone hydrochloride extended-release tablets are not indicated as an as-needed (prn) analgesic. (1)

2 DOSAGE AND ADMINISTRATION

- Hydromorphone hydrochloride extended-release tablets should be prescribed only by healthcare professionals who are knowledgeable about the use of extended-release/long-acting opioids and how to mitigate the associated risks. (2.1)
- Use the lowest effective dosage for the shortest duration of time consistent with individual patient treatment goals. Reserve titration to higher doses of hydromorphone hydrochloride extended-release tablets for patients in whom lower doses are insufficiently effective and in whom the expected benefits of using a higher dose opioid clearly outweigh the substantial risks. (2.1, 5)
- Initiate the dosing regimen for each patient individually, taking into account the patient’s underlying cause and severity of pain, prior analgesic treatment and response, and risk factors for addiction, abuse, and misuse. (5.1)
- Respiratory depression can occur at any time during opioid therapy, especially when initiating and following dosage increases with hydromorphone hydrochloride extended-release tablets. Consider this risk when selecting an initial dose and when making dose adjustments (2.1, 5.2).
- For once daily administration IN OPIOID-TOLERANT PATIENTS. (2.1)
- Instruct patients to swallow hydromorphone hydrochloride extended-release tablets intact, and not to cut, break, chew, crush, or dissolve the tablets (risk of potentially fatal overdose). (2.1, 5.1)
- Discuss opioid overdose reversal agents and options for acquiring them with the patient and/or caregiver, both when initiating and renewing treatment with hydromorphone hydrochloride extended-release tablets, especially if the patient has additional risk factors for overdose, or close contacts at risk for exposure and overdose. (2.2, 5.1, 5.2, 5.3)
- Dose may be increased using increments of 4 to 8 mg every 3 to 4 days as needed to achieve adequate analgesia. (2.4)
- Periodically reassess patients receiving hydromorphone hydrochloride extended-release tablets to evaluate the continued need for opioid analgesics to maintain pain control for the signs or symptoms of adverse reactions, and for the development of addiction, abuse, or misuse. (2.4)
- Do not rapidly reduce or abruptly discontinue hydromorphone hydrochloride extended-release tablets in a physically-dependent patient because rapid reduction or abrupt discontinuation of opioid analgesics has resulted in serious withdrawal symptoms, uncontrolled pain, and suicide. (2.5, 5.13)
- Moderate Hepatic Impairment: Initiate treatment with 25% of the dose that would be prescribed for patients with normal hepatic function. Monitor closely for respiratory and central nervous system depression. (2.6)
- Moderate and Severe Renal Impairment: Initiate treatment in patients with moderate renal impairment with 50% and patients with severe renal impairment with 25% of the hydromorphone hydrochloride extended-release tablets dose that would be prescribed for patients with normal renal function. Monitor closely for respiratory and central nervous system depression. (2.7)

3 DOSAGE FORMS AND STRENGTHS

- Extended-release tablets: 8 mg, 12 mg, 16 mg, 24 mg, 32 mg (3)

4 CONTRAINDICATIONS

- Opioid non-tolerant patients (4)
- Significant respiratory depression (4)
- Acute or severe bronchial asthma in an unmonitored setting or in absence of resuscitative equipment (4)
- Known or suspected gastrointestinal obstruction, including paralytic ileus (4)
- Narrowed or obstructed gastrointestinal tract (4)
- Known hypersensitivity to any components including hydromorphone hydrochloride and sulfites (4, 5.14)

5 WARNINGS AND PRECAUTIONS

- Opioid-Induced Hyperalgesia and Allodynia: Opioid-Induced Hyperalgesia (OIH) occurs when an opioid analgesic paradoxically causes an increase in pain, or an increase in sensitivity to pain. If OIH is suspected, carefully consider appropriately decreasing the dose of the current opioid analgesic or opioid rotation. (5.6)
- Life-Threatening Respiratory Depression in Patients with Chronic Pulmonary Disease or Elderly Cachectic Debilitated Patients: Regularly evaluate closely, particularly during initiation and titration. (5.7)
- Adrenal Insufficiency: If diagnosed, treat with physiologic replacement of corticosteroids, and wean patient off of the opioid. (5.8)
- Severe Hypotension: Regularly evaluate during dose initiation and titration. Avoid use of hydromorphone hydrochloride extended-release tablets in patients with circulatory shock. (5.9)
- Risks of Use in Patients with Increased Intracranial Pressure, Brain, Tumors, Head Injury, or Impaired Consciousness: Monitor for sedation and respiratory depression. Avoid use of hydromorphone hydrochloride extended-release tablets in patients with impaired consciousness or coma. (5.10)

6 ADVERSE REACTIONS

Most common adverse reactions (incidence >10%) are: constipation, nausea, vomiting, somnolence, headache, and dizziness. (6.1)

To report SUSPECTED ADVERSE REACTIONS, contact Trigen Laboratories, LLC at 1-800-444-5164 or FDA at 1-800-FDA-1088 or www.fda.gov/medwatch.

7 DRUG INTERACTIONS

- Serotonergic Drugs: Concomitant use may result in serotonin syndrome. Discontinue hydromorphone hydrochloride extended-release tablets if serotonin syndrome is suspected. (7)
- Monoamine Oxidase Inhibitors (MAOIs): Can potentiate the effects of hydromorphone. Avoid concomitant use in patients receiving MAOIs or within 14 days of stopping treatment with an MAOI. (7)
- Mixed agonist/antagonist and partial agonist opioid analgesics: Avoid use with hydromorphone hydrochloride extended-release tablets because they may reduce analgesic effect of hydromorphone hydrochloride extended-release tablets or precipitate withdrawal symptoms. (5.13, 7)

8 USE IN SPECIFIC POPULATIONS

- Pregnancy: May cause fetal harm. (8.1)
- Lactation: Not recommended. (8.2)
- Severe Hepatic Impairment: Use not recommended. (8.6)
- Severe Renal Impairment: Consider an alternate analgesic. (8.7)

FULL PRESCRIBING INFORMATION

WARNING: SERIOUS AND LIFE-THREATENING RISKS FROM USE OF HYDROMORPHONE HYDROCHLORIDE EXTENDED-RELEASE TABLETS

Addiction, Abuse, and Misuse

Because the use of hydromorphone hydrochloride extended-release tablets exposes patients and other users to the risks of opioid addiction, abuse, and misuse, which can lead to overdose and death, assess each patient’s risk prior to prescribing and reassess all patients regularly for the development of these behaviors and conditions [see Warnings and Precautions (5.1)].

Life-Threatening Respiratory Depression

Serious, life-threatening, or fatal respiratory depression may occur with use of hydromorphone hydrochloride extended-release tablets, especially during initiation or following a dosage increase. To reduce the risk of respiratory depression, proper dosing and titration of hydromorphone hydrochloride extended-release tablets are essential. Instruct patients to swallow hydromorphone hydrochloride extended-release tablets whole to avoid exposure to a potentially fatal dose of hydromorphone [see Warnings and Precautions (5.2)].

Accidental Ingestion

Accidental ingestion of even one dose of hydromorphone hydrochloride extended-release tablets, especially by children, can result in a fatal overdose of hydromorphone [see Warnings and Precautions (5.2)].

Risks From Concomitant Use With Benzodiazepines Or Other CNS Depressants

Concomitant use of opioids with benzodiazepines or other central nervous system (CNS) depressants, including alcohol, may result in profound sedation, respiratory depression, coma, and death. Reserve concomitant prescribing of hydromorphone hydrochloride extended-release tablets and benzodiazepines or other CNS depressants for use in patients for whom alternative treatment options are inadequate [see Warnings and Precautions (5.3), Drug Interactions (7)].

Neonatal Opioid Withdrawal Syndrome (NOWS)

Advise pregnant women using opioids for an extended period of time of the risk of Neonatal Opioid Withdrawal Syndrome, which may be life-threatening if not recognized and treated. Ensure that management by neonatology experts will be available at delivery [see Warnings and Precautions (5.4)].

Opioid Analgesic Risk Evaluation and Mitigation Strategy (REMS):

Healthcare providers are strongly encouraged to complete a REMS-compliant education program and to counsel patients and caregivers on serious risks, safe use, and the importance of reading the Medication Guide with each prescription [see Warnings and Precautions (5.5)].

1 INDICATIONS AND USAGE

Hydromorphone hydrochloride extended-release tablets are indicated in opioid-tolerant patients for the management of severe and persistent pain that requires an opioid analgesic and that cannot be adequately treated with alternative options, including immediate-release opioids.

Patients considered opioid tolerant are those who are receiving, for one week or longer, at least 60 mg oral morphine per day, 25 mcg transdermal fentanyl per hour, 30 mg oral oxycodone per day, 8 mg oral hydromorphone per day, 25 mg oral oxymorphone per day, 60 mg oral hydrocodone per day, or an equianalgesic dose of another opioid.

Limitations of Use

- Because of the risks of addiction, abuse, misuse, overdose, and death, which can occur at any dosage or duration and persist over the course of therapy [see Warnings and Precautions (5.1)], reserve opioid analgesics, including hydromorphone hydrochloride extended-release tablets for use in patients for whom alternative treatment options are ineffective, not tolerated, or would be otherwise inadequate to provide sufficient management of pain.
- Hydromorphone hydrochloride extended-release tablets are not indicated as an as-needed (prn) analgesic.

2 DOSAGE AND ADMINISTRATION

2.1 Important Dosage and Administration Information

To avoid medication errors, prescribers and pharmacists must be aware that hydromorphone is available as both immediate-release 8 mg tablets and extended-release 8 mg tablets.

Hydromorphone hydrochloride extended-release tablets should be prescribed only by healthcare professionals who are knowledgeable about the use of extended-release/long-acting opioids and how to mitigate the associated risks.

Due to the risk of respiratory depression, hydromorphone hydrochloride extended-release tablets are only indicated for use in patients who are already opioid-tolerant. Discontinue or taper all other extended-release opioids when beginning hydromorphone hydrochloride extended-release tablets therapy. As hydromorphone hydrochloride extended-release tablets are only for use in opioid-tolerant patients, do not begin any patient on hydromorphone hydrochloride extended-release tablets as the first opioid.

Patients who are opioid-tolerant are those receiving, for one week or longer, at least 60 mg of oral morphine per day, at least 25 mcg transdermal fentanyl per hour, at least 30 mg of oral oxycodone per day, at least 8 mg of oral hydromorphone per day, at least 25 mg oral oxymorphone per day, at least 60 mg oral hydrocodone per day, or an equianalgesic dose of another opioid.

- Use the lowest effective dosage for the shortest duration of time consistent with individual patient treatment goals [see Warnings and Precautions (5)]. Because the risk of overdose increases as opioid doses increase, reserve titration to higher doses of hydromorphone hydrochloride extended-release tablets for patients in whom lower doses are insufficiently effective and in whom the expected benefits of using a higher dose opioid clearly outweigh the substantial risks.
- Initiate the dosing regimen for each patient individually, taking into account the patient's underlying cause and prior analgesic treatment and response, and risk factors for addiction, abuse, and misuse [see Warnings and Precautions (5.1)].
- Respiratory depression can occur at any time during opioid therapy, especially when initiating and following dosage increases with hydromorphone hydrochloride extended-release tablets. Consider this risk when selecting an initial dose and when making dose adjustments [see Warnings and Precautions (5)].
- Hydromorphone hydrochloride extended-release tablets are administered orally once daily IN OPIOID-TOLERANT PATIENTS.
- Instruct patients to swallow hydromorphone hydrochloride extended-release tablets whole [see Patient Counseling Information (17)]. Crushing, chewing, or dissolving hydromorphone hydrochloride extended-release tablets will result in uncontrolled delivery of hydromorphone and can lead to overdose or death [see Warnings and Precautions (5.1)].

2.2 Patient Access to an Opioid Overdose Reversal Agent for the Emergency Treatment of Opioid Overdose

Inform patients and caregivers about opioid overdose reversal agents (e.g., naloxone, nalmefene). Discuss the importance of having access to an opioid overdose reversal agent, especially if the patient has risk factors for overdose (e.g., concomitant use of CNS depressants, a history of opioid use disorder, or prior opioid overdose) or if there are household members (including children) or other close contacts at risk for accidental ingestion or opioid overdose. The presence of risk factors for overdose should not prevent the management of pain in any patient [see Warnings and Precautions (5.1, 5.2, 5.3).

Discuss the options for obtaining an opioid overdose reversal agent (e.g., prescription, over-the-counter, or as part of a community-based program) [see Warnings and Precautions (5.2)].

There are important differences among the opioid overdose reversal agents, such as route of administration, product strength, approved patient age range, and pharmacokinetics. Be familiar with these differences, as outlined in the approved labeling for those products, prior to recommending or prescribing such an agent.

2.3 Initial Dosage

It is safer to underestimate a patient’s 24-hour oral hydromorphone dosage and provide rescue medication (e.g., immediate-release opioid) than to overestimate the 24-hour oral hydromorphone dosage and manage an adverse reaction due to overdose. While useful tables of opioid equivalents are readily available, there is inter-patient variability in the potency of opioid drugs and opioid formulations. Frequently reevaluate patients for signs and symptoms of opioid withdrawal and for signs of oversedation/toxicity after converting patients to hydromorphone hydrochloride extended-release tablets.

Conversion from Other Oral Opioid Analgesics to Hydromorphone Hydrochloride Extended-Release Tablets

When hydromorphone hydrochloride extended-release tablets therapy is initiated, discontinue all opioid analgesics other than those used on an as needed basis for breakthrough pain when appropriate.

In a hydromorphone hydrochloride extended-release tablets clinical trial with an open-label titration period, patients were converted from their prior opioid to hydromorphone hydrochloride extended-release tablets using the Table 1 as a guide for the initial hydromorphone hydrochloride extended-release tablets dose. The recommended starting dose of hydromorphone hydrochloride extended-release tablets is 50% of the calculated estimate of daily hydromorphone requirement. Calculate the estimated daily hydromorphone requirement using Table 1.

Consider the following when using the information in Table 1:

- This is not a table of equianalgesic doses.
- The conversion factors in this table are only for the conversion from one of the listed oral opioid analgesics to hydromorphone hydrochloride extended-release tablets.
- The table cannot be used to convert from hydromorphone hydrochloride extended-release tablets to another opioid. Doing so will result in an overestimation of the dose of the new opioid and may result in fatal overdose.

Table 1.

Conversion Factors to Hydromorphone Hydrochloride Extended-Release Tablets

To calculate the estimated hydromorphone hydrochloride extended-release tablets dose using Table 1:

- For patients on a single opioid, sum the current total daily dose of the opioid and then multiply the total daily dose by the conversion factor to calculate the approximate oral hydromorphone daily dose.
- For patients on a regimen of more than one opioid, calculate the approximate oral hydromorphone dose for each opioid and sum the totals to obtain the approximate total hydromorphone daily dose.
- For patients on a regimen of fixed-ratio opioid/non-opioid analgesic products, use only the opioid component of these products in the conversion.

Always round the dose down, if necessary, to the appropriate hydromorphone hydrochloride extended-release tablets strength(s) available.

Example conversion from a single opioid to hydromorphone hydrochloride extended-release tablets:

Step 1: Sum the total daily dose of the opioid

- 30 mg of oxycodone 2 times daily = 60 mg total daily dose of oxycodone

Step 2: Calculate the approximate equivalent dose of oral hydromorphone based on the total daily dose of the current opioid using Table 1

- 60 mg total daily dose of oxycodone x Conversion Factor of 0.4 = 24 mg of oral hydromorphone daily

Step 3: Calculate the approximate starting dose of hydromorphone hydrochloride extended-release tablets to be given every 24 hours, which is 50% of the calculated oral hydromorphone dose. Round down, if necessary, to the appropriate hydromorphone hydrochloride extended-release tablets strengths available.

- 50% of 24 mg results in an initial dose of 12 mg of hydromorphone hydrochloride extended-release tablets once daily
- Adjust individually for each patient

Close observation and frequent titration are warranted until pain management is stable on the new opioid.

Conversion from Methadone to Hydromorphone Hydrochloride Extended-Release Tablets

Close monitoring is of particular importance when converting from methadone to other opioid agonists. The ratio between methadone and other opioid agonists may vary widely as a function of previous dose exposure. Methadone has a long half-life and can accumulate in the plasma.

Conversion from Fentanyl Transdermal System to Hydromorphone Hydrochloride Extended-Release Tablets

Eighteen hours following the removal of the fentanyl transdermal system, hydromorphone hydrochloride extended-release tablets treatment can be initiated. To calculate the 24-hour hydromorphone hydrochloride extended-release tablets dose, use a conversion factor of 25 mcg/hr fentanyl transdermal system to 12 mg of hydromorphone hydrochloride extended-release tablets. Then reduce the hydromorphone hydrochloride extended-release tablets dose by 50%.

For example:

Step 1: Identify the dose of transdermal fentanyl.

- 75 mg of transdermal fentanyl

Step 2: Use the conversion factor of 25 mcg/hr fentanyl transdermal system to 12 mg of hydromorphone hydrochloride extended-release tablets.

- 75 mg of transdermal fentanyl: 36 mg total daily dose of hydromorphone hydrochloride extended-release tablets

Step 3: Calculate the approximate starting dose of hydromorphone hydrochloride extended-release tablets to be given every 24 hours, which is 50% of the converted dose. Round down, if necessary, to the appropriate hydromorphone hydrochloride extended-release tablets strengths available.

- 50% of 36 mg results in an initial dose of 18 mg, which would be rounded down to 16 mg of hydromorphone hydrochloride extended-release tablets once daily
- Adjust individually for each patient

2.4 Titration and Maintenance of Therapy

Individually titrate hydromorphone hydrochloride extended-release tablets to a dose that provides adequate analgesia and minimizes adverse reactions. Continually reevaluate patients receiving hydromorphone hydrochloride extended-release tablets to assess the maintenance of pain control, signs and symptoms of opioid withdrawal, and other adverse reactions, as well as to reassess for the development of addiction, abuse, or misuse [see Warnings and Precautions (5.1, 5.13)]. Frequent communication is important among the prescriber, other members of the healthcare team, the patient, and the caregiver/family during periods of changing analgesic requirements, including initial titration. During use of opioid therapy for an extended period of time, periodically reassess the continued need for opioid analgesics.

If after increasing the dosage, unacceptable opioid-related adverse reactions are observed (including an increase in pain after dosage increase), consider reducing the dosage [see Warnings and Precautions (5)]. Adjust the dosage to obtain an appropriate balance between management of pain and opioid-related adverse reactions.

Plasma levels of hydromorphone hydrochloride extended-release tablets are sustained for 18 to 24 hours. Dosage adjustments of hydromorphone hydrochloride extended-release tablets may be made in increments of 4 to 8 mg every 3 to 4 days as needed to achieve adequate analgesia.

Patients who experience breakthrough pain may require a dose increase of hydromorphone hydrochloride extended-release tablets, or may need rescue medication with an appropriate dose of an immediate-release analgesic. If the level of pain increases after dose stabilization, attempt to identify the source of increased pain before increasing the hydromorphone hydrochloride extended-release tablets dose.

If unacceptable opioid-related adverse reactions are observed, the subsequent doses may be reduced. Adjust the dose to obtain an appropriate balance between management of pain and opioid-related adverse reactions.

2.5 Safe Reduction or Discontinuation of Hydromorphone Hydrochloride Extended-Release Tablets

Do not rapidly reduce or abruptly discontinue hydromorphone hydrochloride extended-release tablets in patients who may be physically dependent on opioids. Rapid reduction or abrupt discontinuation of opioid analgesics in patients who are physically dependent on opioids has resulted in serious withdrawal symptoms, uncontrolled pain, and suicide. Rapid reduction or abrupt discontinuation has also been associated with attempts to find other sources of opioid analgesics, which may be confused with drug seeking for abuse. Patients may also attempt to treat their pain or withdrawal symptoms with illicit opioids, such as heroin, and other substances.

When a decision has been made to decrease the dose or discontinue therapy in an opioid-dependent patient taking hydromorphone hydrochloride extended-release tablets, there are a variety of factors that should be considered, including the total daily dose of opioid (including hydromorphone hydrochloride extended-release tablets) the patient has been taking, the duration of treatment, the type of pain being treated, and the physical and psychological attributes of the patient. It is important to ensure ongoing care of the patient and to agree on an appropriate tapering schedule and follow-up plan so that patient and provider goals and expectations are clear and realistic. When opioid analgesics are being discontinued due to a suspected substance use disorder, evaluate and treat the patient, or refer for evaluation and treatment of the substance use disorder. Treatment should include evidence-based approaches, such as medication assisted treatment of opioid use disorder. Complex patients with comorbid pain and substance use disorders may benefit from referral to a specialist.

There are no standard opioid tapering schedules that are suitable for all patients. Good clinical practice dictates a patient-specific plan to taper the dose of the opioid gradually. For patients on hydromorphone hydrochloride extended-release tablets who are physically opioid-dependent, initiate the taper by a small enough increment (e.g., no greater than 10% to 25% of the total daily dose) to avoid withdrawal symptoms, and proceed with dose-lowering at an interval of every 2 to 4 weeks. Patients who have been taking opioids for briefer periods of time may tolerate a more rapid taper.

It may be necessary to provide the patient with lower dosage strengths to accomplish a successful taper. Reassess the patient frequently to manage pain and withdrawal symptoms, should they emerge. Common withdrawal symptoms include restlessness, lacrimation, rhinorrhea, yawning, perspiration, chills, myalgia, and mydriasis. Other signs and symptoms also may develop, including irritability, anxiety, backache, joint pain, weakness, abdominal cramps, insomnia, nausea, anorexia, vomiting, diarrhea, or increased blood pressure, respiratory rate, or heart rate. If withdrawal symptoms arise, it may be necessary to pause the taper for a period of time or raise the dose of the opioid analgesic to the previous dose, and then proceed with a slower taper. In addition, evaluate patients for any changes in mood, emergence of suicidal thoughts, or use of other substances.

When managing patients taking opioid analgesics, particularly those who have been treated for an extended period of time, and/or with high doses for chronic pain, ensure that a multimodal approach to pain management, including mental health support (if needed), is in place prior to initiating an opioid analgesic taper. A multimodal approach to pain management may optimize the treatment of chronic pain, as well as assist with the successful tapering of the opioid analgesic [see Warnings and Precautions (5.13), Drug Abuse and Dependence (9.3)].

2.6 Dosage Modifications in Patients with Moderate Hepatic Impairment

Start patients with moderate hepatic impairment on 25% of the hydromorphone hydrochloride extended-release tablets dose that would be prescribed for patients with normal hepatic function. Closely monitor patients with moderate hepatic impairment for respiratory and central nervous system depression during initiation of therapy with hydromorphone hydrochloride extended-release tablets and during dose titration. Use of alternate analgesics is recommended for patients with severe hepatic impairment [see Use in Specific Populations (8.6)].

2.7 Dosage Modifications in Patients with Renal Impairment

Start patients with moderate renal impairment on 50% of the hydromorphone hydrochloride extended-release tablets dose that would be prescribed for patients with normal renal function. Closely monitor patients with renal impairment for respiratory and central nervous system depression during initiation of therapy with hydromorphone hydrochloride extended-release tablets and during dose titration. As hydromorphone hydrochloride extended-release tablets are only intended for once daily administration, consider use of an alternate analgesic that may permit more flexibility with the dosing interval in patients with severe renal impairment [see Use in Specific Populations (8.7)].

3 DOSAGE FORMS AND STRENGTHS

Hydromorphone hydrochloride extended-release tablets are available in 8 mg, 12 mg, 16 mg, 24 mg, or 32 mg dosage strengths. The 8 mg tablets are round, biconvex, pink tablets imprinted with "OS 211" on one side. The 12 mg tablets are round, biconvex, yellow tablets imprinted with "OS 212" on one side. The 16 mg tablets are round, biconvex, yellow tablets imprinted with "OS 213" on one side. The 24 mg tablets are round, biconvex, gray tablets imprinted with "OS 216" on one side. The 32 mg tablets are round, biconvex, white tablets imprinted with "OS 214" on one side.

4 CONTRAINDICATIONS

Hydromorphone hydrochloride extended-release tablets are contraindicated in:

- Opioid non-tolerant patients. Fatal respiratory depression could occur in patients who are not opioid tolerant.
- Patients with significant respiratory depression [see Warnings and Precautions (5.2)].
- Acute or severe bronchial asthma in an unmonitored setting or in the absence of resuscitative equipment [see Warnings and Precautions (5.7)].
- Known or suspected gastrointestinal obstruction, including paralytic ileus [see Warnings and Precautions (5.11)].
- Patients who have had surgical procedures and/or underlying disease resulting in narrowing of the gastrointestinal tract, or have “blind loops” of the gastrointestinal tract or gastrointestinal obstruction [see Warnings and Precautions (5.11)].
- Patients with hypersensitivity (e.g., anaphylaxis) to hydromorphone [see Warnings and Precautions (5.14)].

5 WARNINGS AND PRECAUTIONS

5.1 Addiction, Abuse, and Misuse

Hydromorphone hydrochloride extended-release tablets contain hydromorphone, a Schedule II controlled substance. As an opioid, hydromorphone hydrochloride extended-release tablets exposes users to the risks of addiction, abuse, and misuse [see Drug Abuse and Dependence (9)].

Although the risk of addiction in any individual is unknown, it can occur in patients appropriately prescribed hydromorphone hydrochloride extended-release tablets and in those who obtain the drug illicitly. Addiction can occur at recommended doses and if the drug is misused or abused. The risk of opioid-related overdose or overdose-related death is increased with higher opioid doses, and this risk persists over the course of therapy. In postmarketing studies, addiction, abuse, misuse, and fatal and non-fatal opioid overdose were observed in patients with long-term opioid use [see Adverse Reactions (6.2)].

Assess each patient’s risk for opioid addiction, abuse, or misuse prior to prescribing hydromorphone hydrochloride extended-release tablets, and reassess all patients receiving hydromorphone hydrochloride extended-release tablets for the development of these behaviors and conditions. Risks are increased in patients with a personal or family history of substance abuse (including drug or alcohol addiction or abuse) or mental illness (e.g., major depression). The potential for these risks should not, however, prevent the prescribing of hydromorphone hydrochloride extended-release tablets for the proper management of pain in any given patient. Patients at increased risk may be prescribed opioids such as hydromorphone hydrochloride extended-release tablets, but use in such patients necessitates intensive counseling about the risks and proper use of hydromorphone hydrochloride extended-release tablets along with frequent reevaluation for signs of addiction, abuse, and misuse. Consider recommending or prescribing an opioid overdose reversal agent [see Dosage and Administration (2.2), Warnings and Precautions (5.2)].

Abuse or misuse of hydromorphone hydrochloride extended-release tablets by crushing, chewing, snorting, or injecting the dissolved product will result in the uncontrolled delivery of hydromorphone and can result in overdose and death [see Overdosage (10)].

Opioids are sought for non-medical use and are subject to diversion from legitimate prescribed use. Consider these risks when prescribing or dispensing hydromorphone hydrochloride extended-release tablets. Strategies to reduce these risks include prescribing the drug in the smallest appropriate quantity and advising the patient on careful storage of the drug during the course of treatment and proper disposal of unused drug. Contact local state professional licensing board or state-controlled substances authority for information on how to prevent and detect abuse or diversion of this product.

5.2 Life-Threatening Respiratory Depression

Serious, life-threatening, or fatal respiratory depression has been reported with the use of modified-release opioids, even when used as recommended. Respiratory depression from opioid use, if not immediately recognized and treated, may lead to respiratory arrest and death. Management of respiratory depression may include close observation, supportive measures, and use of opioid overdose reversal agents, depending on the patient’s clinical status [see Overdosage (10)]. Carbon dioxide (CO2) retention from opioid-induced respiratory depression can exacerbate the sedating effects of opioids.

While serious, life-threatening, or fatal respiratory depression can occur at any time during the use of hydromorphone hydrochloride extended-release tablets, the risk is greatest during the initiation of therapy or following a dosage increase.

To reduce the risk of respiratory depression, proper dosing and titration of hydromorphone hydrochloride extended-release tablets are essential [see Dosage and Administration (2)]. Overestimating the hydromorphone hydrochloride extended-release tablets dose when converting patients from another opioid product can result in fatal overdose with the first dose.

Accidental ingestion of even one dose of hydromorphone hydrochloride extended-release tablets, especially by children, can result in respiratory depression and death due to an overdose of hydromorphone.

Educate patients and caregivers on how to recognize respiratory depression and emphasize the importance of calling 911 or getting emergency medical help right away in the event of a known or suspected overdose [see Patient Counseling Information (17)].

Opioids can cause sleep-related breathing disorders including central sleep apnea (CSA) and sleep-related hypoxemia. Opioid use increases the risk of CSA in a dose-dependent fashion. In patients who present with CSA, consider decreasing the opioid dosage using best practices for opioid taper [see Dosage and Administration (2.5)].

Patient Access to an Opioid Overdose Reversal Agent for the Emergency Treatment of Opioid Overdose

Inform patients and caregivers about opioid overdose reversal agents (e.g., naloxone, nalmefene). Discuss the importance of having access to an opioid overdose reversal agent, especially if the patient has risk factors for overdose (e.g., concomitant use of CNS depressants, a history of opioid use disorder, or prior opioid overdose) or if there are household members (including children) or other close contacts at risk for accidental ingestion or opioid overdose. The presence of risk factors for overdose should not prevent the management of pain in any patient [see Warnings and Precautions (5.1, 5.3)].

Discuss the options for obtaining an opioid overdose reversal agent (e.g., prescription, over-the-counter, or as part of a community-based program).

There are important differences among the opioid overdose reversal agents, such as route of administration, product strength, approved patient age range, and pharmacokinetics. Be familiar with these differences, as outlined in the approved labeling for those products, prior to recommending or prescribing such an agent.

Educate patients and caregivers on how to recognize respiratory depression, and how to use an opioid overdose reversal agent for the emergency treatment of opioid overdose. Emphasize the importance of calling 911 or getting emergency medical help, even if an opioid overdose reversal agent is administered [see Dosage and Administration (2.2), Warnings and Precautions (5.1, 5.3), Overdosage (10)].

5.3 Risks from Concomitant Use with Benzodiazepines or Other CNS Depressants

Profound sedation, respiratory depression, coma, and death may result from the concomitant use of hydromorphone hydrochloride extended-release tablets with benzodiazepines and/or other CNS depressants, including alcohol (e.g., non-benzodiazepine sedatives/hypnotics, anxiolytics, tranquilizers, muscle relaxants, general anesthetics, antipsychotics, gabapentinoids [gabapentin or pregabalin], and other opioids). Because of these risks, reserve concomitant prescribing of these drugs for use in patients for whom alternative treatment options are inadequate.

Observational studies have demonstrated that concomitant use of opioid analgesics and benzodiazepines increases the risk of drug-related mortality compared to use of opioid analgesics alone. Because of similar pharmacological properties, it is reasonable to expect similar risk with the concomitant use of other CNS depressant drugs with opioid analgesics [see Drug Interactions (7)].

If the decision is made to prescribe a benzodiazepine or other CNS depressant concomitantly with an opioid analgesic, prescribe the lowest effective dosages and minimum durations of concomitant use. In patients already receiving an opioid analgesic, prescribe a lower initial dose of the benzodiazepine or other CNS depressant than indicated in the absence of an opioid, and titrate based on clinical response. If an opioid analgesic is initiated in a patient already taking a benzodiazepine or other CNS depressant, prescribe a lower initial dose of the opioid analgesic, and titrate based on clinical response. Inform patients and caregivers of this potential interaction, educate them on the signs and symptoms of respiratory depression (including sedation).

If concomitant use is warranted, consider recommending or prescribing an opioid overdose reversal agent [see Dosage and Administration (2.2), Warnings and Precautions (5.2)].

Advise both patients and caregivers about the risks of respiratory depression and sedation when hydromorphone hydrochloride extended-release tablets are used with benzodiazepines or other CNS depressants (including alcohol and illicit drugs). Advise patients not to drive or operate heavy machinery until the effects of concomitant use of the benzodiazepine or other CNS depressant have been determined. Screen patients for risk of substance use disorders, including opioid abuse and misuse, and warn them of the risk for overdose and death associated with the use of additional CNS depressants including alcohol and illicit drugs [see Drug Interactions (7), Patient Counseling Information (17)].

5.4 Neonatal Opioid Withdrawal Syndrome

Use of hydromorphone hydrochloride extended-release tablets for an extended period of time during pregnancy can result in withdrawal in the neonate. Neonatal opioid withdrawal syndrome, unlike opioid withdrawal syndrome in adults, may be life-threatening if not recognized and treated, and requires management according to protocols developed by neonatology experts. Observe newborns for signs of neonatal opioid withdrawal syndrome and manage accordingly. Advise pregnant women using opioids for an extended period of time of the risk of neonatal opioid withdrawal syndrome and ensure that appropriate treatment will be available [see Use in Specific Populations (8.1), Patient Counseling Information (17)].

5.5 Risk Evaluation and Mitigation Strategy (REMS)

To ensure that the benefits of opioid analgesics outweigh the risks of addiction, abuse, and misuse, the Food and Drug Administration (FDA) has required a Risk Evaluation and Mitigation Strategy (REMS) for these products. Under the requirements of the REMS, drug companies with approved opioid analgesic products must make REMS-compliant education programs available to healthcare providers. Healthcare providers are strongly encouraged to do all of the following:

- Complete a REMS-compliant education program offered by an accredited provider of continuing education (CE) or another education program that includes all the elements of the FDA Education Blueprint for Health Care Providers Involved in the Management or Support of Patients with Pain.
- Discuss the safe use, serious risks, and proper storage and disposal of opioid analgesics with patients and/or their caregivers every time these medicines are prescribed. The Patient Counseling Guide (PCG) can be obtained at this link: www.fda.gov/OpioidAnalgesicREMSPCG.
- Emphasize to patients and their caregivers the importance of reading the Medication Guide that they will receive from their pharmacist every time an opioid analgesic is dispensed to them.
- Consider using other tools to improve patient, household, and community safety, such as patient prescriber agreements that reinforce patient-prescriber responsibilities.

To obtain further information on the opioid analgesic REMS and for a list of accredited REMS CME/CE, call 1-800-503-0784, or log on to www.opioidanalgesicrems.com. The FDA Blueprint can be found at www.fda.gov/OpioidAnalgesicREMSBlueprint.

5.6 Opioid-Induced Hyperalgesia and Allodynia

Opioid-Induced Hyperalgesia (OIH) occurs when an opioid analgesic paradoxically causes an increase in pain, or an increase in sensitivity to pain. This condition differs from tolerance, which is the need for increasing doses of opioids to maintain a defined effect [see Dependence (9.3)]. Symptoms of OIH include (but may not be limited to) increased levels of pain upon opioid dosage increase, decreased levels of pain upon opioid dosage decrease, or pain from ordinarily non-painful stimuli (allodynia). These symptoms may suggest OIH only if there is no evidence of underlying disease progression, opioid tolerance, opioid withdrawal, or addictive behavior.

Cases of OIH have been reported, both with short-term and longer-term use of opioid analgesics. Though the mechanism of OIH is not fully understood, multiple biochemical pathways have been implicated. Medical literature suggests a strong biologic plausibility between opioid analgesics and OIH and allodynia. If a patient is suspected to be experiencing OIH, carefully consider appropriately decreasing the dose of the current opioid analgesic or opioid rotation (safety switching the patient to a different opioid moiety) [see Dosage and Administration (2.1); Warnings and Precautions (5.13)].

5.7 Life-Threatening Respiratory Depression in Patients with Chronic Pulmonary Disease or in Elderly, Cachectic, or Debilitated Patients

The use of hydromorphone hydrochloride extended-release tablets in patients with acute or severe bronchial asthma in an unmonitored setting or in the absence of resuscitative equipment is contraindicated.

Patients with Chronic Pulmonary Disease: hydromorphone hydrochloride extended-release tablets treated patients with significant chronic obstructive pulmonary disease or cor pulmonale, and those with a substantially decreased respiratory reserve, hypoxia, hypercapnia, or pre-existing respiratory depression are at increased risk of decreased respiratory drive including apnea, even at recommended dosages of hydromorphone hydrochloride extended-release tablets [see Warnings and Precautions (5.2)].

Elderly, Cachectic, or Debilitated Patients: Life-threatening respiratory depression is more likely to occur in elderly, cachectic, or debilitated patients because they may have altered pharmacokinetics or altered clearance compared to younger, healthier patients [see Warnings and Precautions (5.2)].

Regularly evaluate patients, particularly when initiating and titrating hydromorphone hydrochloride extended-release tablets and when hydromorphone hydrochloride extended-release tablets are given concomitantly with other drugs that depress respiration [see Warnings and Precautions (5), Drug Interactions (7)]. Alternatively, consider the use of non-opioid analgesics in these patients.

5.8 Adrenal Insufficiency

Cases of adrenal insufficiency have been reported with opioid use, more often following greater than one month of use. Presentation of adrenal insufficiency may include non-specific symptoms and signs including nausea, vomiting, anorexia, fatigue, weakness, dizziness, and low blood pressure. If adrenal insufficiency is suspected, confirm the diagnosis with diagnostic testing as soon as possible. If adrenal insufficiency is diagnosed, treat with physiologic replacement doses of corticosteroids. Wean the patient off of the opioid to allow adrenal function to recover and continue corticosteroid treatment until adrenal function recovers. Other opioids may be tried as some cases reported use of a different opioid without recurrence of adrenal insufficiency. The information available does not identify any particular opioids as being more likely to be associated with adrenal insufficiency.

5.9 Severe Hypotension

Hydromorphone hydrochloride extended-release tablets may cause severe hypotension including orthostatic hypotension and syncope in ambulatory patients. There is an increased risk in patients whose ability to maintain blood pressure has already been compromised by a reduced blood volume, or concurrent administration of certain CNS depressant drugs (e.g., phenothiazines or general anesthetics) [see Drug Interactions (7)]. Regularly evaluate these patients for signs of hypotension after initiating or titrating the dosage of hydromorphone hydrochloride extended-release tablets. In patients with circulatory shock, hydromorphone hydrochloride extended-release tablets may cause vasodilation that can further reduce cardiac output and blood pressure. Avoid the use of hydromorphone hydrochloride extended-release tablets in patients with circulatory shock.

5.10 Risks of Use in Patients with Increased Intracranial Pressure, Brain Tumors, Head Injury, or Impaired Consciousness

In patients who may be susceptible to the intracranial effects of CO2 retention (e.g., those with evidence of increased intracranial pressure or brain tumors), hydromorphone hydrochloride extended-release tablets may reduce respiratory drive, and the resultant CO2 retention can further increase intracranial pressure. Regularly evaluate such patients for signs of sedation and respiratory depression, particularly when initiating therapy with hydromorphone hydrochloride extended-release tablets.

Opioids may also obscure the clinical course in a patient with a head injury. Avoid the use of hydromorphone hydrochloride extended-release tablets in patients with impaired consciousness or coma.

5.11 Risk of Gastrointestinal Complications

Hydromorphone hydrochloride extended-release tablets are contraindicated in patients with known or suspected gastrointestinal obstruction, including paralytic ileus. Avoid the use of hydromorphone hydrochloride extended-release tablets in patients with other GI obstruction.

Because the hydromorphone hydrochloride extended-release tablets are nondeformable and does not appreciably change in shape in the GI tract, hydromorphone hydrochloride extended-release tablets are contraindicated in patients with preexisting severe gastrointestinal narrowing (pathologic or iatrogenic, for example: esophageal motility disorders, small bowel inflammatory disease, “short gut” syndrome due to adhesions or decreased transit time, past history of peritonitis, cystic fibrosis, chronic intestinal pseudoobstruction, or Meckel’s diverticulum). There have been reports of obstructive symptoms in patients with known strictures or risk of strictures, such as previous GI surgery, in association with the ingestion of drugs in nondeformable extended-release formulations.

It is possible that hydromorphone hydrochloride extended-release tablets may be visible on abdominal x-rays under certain circumstances, especially when digital enhancing techniques are utilized.

The hydromorphone in hydromorphone hydrochloride extended-release tablets may cause spasm of the sphincter of Oddi. Opioids may cause increases in serum amylase. Regularly evaluate patients with biliary tract disease, including acute pancreatitis, for worsening symptoms.

Cases of opioid-induced esophageal dysfunction (OIED) have been reported in patients taking opioids. The risk of OIED may increase as the dose and/or duration of opioids increases. Regularly evaluate patients for signs and symptoms of OIED (e.g., dysphagia, regurgitation, non-cardiac chest pain), and if necessary, adjust opioid therapy as clinically appropriate [see Clinical Pharmacology (12.2)].

5.12 Increased Risk of Seizures in Patients with Seizure Disorders

The hydromorphone in hydromorphone hydrochloride extended-release tablets may increase the frequency of seizures in patients with seizure disorders, and may increase the risk of seizures occurring in other clinical settings associated with seizures. Regularly evaluate patients with a history of seizure disorders for worsened seizure control during hydromorphone hydrochloride extended-release tablets therapy.

5.13 Withdrawal

Do not rapidly reduce or abruptly discontinue hydromorphone hydrochloride extended-release tablets in a patient physically dependent on opioids. When discontinuing hydromorphone hydrochloride extended-release tablets in a physically dependent patient, gradually taper the dosage. Rapid tapering of hydromorphone in a patient physically dependent on opioids may lead to a withdrawal syndrome and return of pain [see Dosage and Administration (2.5), Drug Abuse and Dependence (9.3)].

Additionally, avoid the use of mixed agonist/antagonist (e.g., pentazocine, nalbuphine, and butorphanol) or partial agonist (e.g., buprenorphine) analgesics in patients who are receiving a full opioid agonist analgesic, including hydromorphone hydrochloride extended-release tablets. In these patients, mixed agonist/antagonist and partial agonist analgesics may reduce the analgesic effect and/or may precipitate withdrawal symptoms [see Drug Interactions (7)].

5.14 Sulfites

Hydromorphone hydrochloride extended-release tablets contain sodium metabisulfite, a sulfite that may cause allergic-type reactions including anaphylactic symptoms and life-threatening or less severe asthmatic episodes in certain susceptible people. The overall prevalence of sulfite sensitivity in the general population is unknown and probably low. Sulfite sensitivity is seen more frequently in asthmatic than in nonasthmatic people [see Adverse Reactions (6.2)].

5.15 Risks of Driving and Operating Machinery

Hydromorphone hydrochloride extended-release tablets may impair the mental and/or physical abilities needed to perform potentially hazardous activities such as driving a car or operating machinery. Warn patients not to drive or operate dangerous machinery unless they are tolerant to the effects of hydromorphone hydrochloride extended-release tablets and know how they will react to the medication [see Patient Counseling Information (17)].

6 ADVERSE REACTIONS

The following serious adverse reactions are discussed elsewhere in the labeling:

- Addiction, Abuse, and Misuse [see Warnings and Precautions (5.1)]
- Life-Threatening Respiratory Depression [see Warnings and Precautions (5.2)]
- Neonatal Opioid Withdrawal Syndrome [see Warnings and Precautions (5.4)]
- Interactions with Benzodiazepine or Other CNS Depressants [see Warnings and Precautions (5.3)]
- Adrenal Insufficiency [see Warnings and Precautions (5.8)]
- Severe Hypotension [see Warnings and Precautions (5.9)]
- Gastrointestinal Adverse Reactions [see Warnings and Precautions (5.11)]
- Seizures [see Warnings and Precautions (5.12)]
- Withdrawal [see Warnings and Precautions (5.13)]
- Opioid-Induced Hyperalgesia and Allodynia [See Warnings and Precautions (5.6)]

6.1 Clinical Trial Experience

Because clinical trials are conducted under widely varying conditions, adverse reaction rates observed in the clinical trials of a drug cannot be directly compared to rates in the clinical trials of another drug and may not reflect the rates observed in clinical practice.

Hydromorphone hydrochloride extended-release tablets were administered to a total of 2,524 patients in 15 controlled and uncontrolled clinical studies. Of these, 423 patients were exposed to hydromorphone hydrochloride extended-release tablets for greater than 6 months and 141 exposed for greater than one year.

The most common adverse reactions leading to study discontinuation were nausea, vomiting, constipation, somnolence, and dizziness. The most common treatment-related serious adverse reactions from controlled and uncontrolled chronic pain studies were drug withdrawal syndrome, overdose, confusional state, and constipation.

The overall incidence of adverse reactions in patients greater than 65 years of age was higher, with a greater than 5% difference in rates for constipation and nausea when compared with younger patients. The overall incidence of adverse reactions in female patients was higher, with a greater than 5% difference in rates for nausea, vomiting, constipation and somnolence when compared with male patients.

A 12-week double-blind, placebo-controlled, randomized withdrawal study was conducted in opioid tolerant patients with moderate to severe low back pain [see Clinical Studies (14)]. A total of 447 patients were enrolled into the open-label titration phase with 268 patients randomized into the double-blind treatment phase. The adverse reactions that were reported in at least 2% of the patients are contained in Table 2.

Table 2.

Number (%) of Patients with Adverse Reactions Reported in ≥ 2% of Patients
with Moderate to Severe Low Back Pain During the Open-Label Titration Phase or Double-Blind Treatment Phase by Preferred Term

The adverse reactions that were reported in at least 2% of the total treated patients (N=2,474) in the 14 chronic clinical trials are contained in Table 3.

Table 3.

Number (%) of Patients with Adverse Reactions Reported in ≥ 2% of Patients
with Chronic Pain Receiving Hydromorphone Hydrochloride Extended-Release Tablets in 14 Clinical Studies by Preferred Term

* Reflux esophagitis, gastroesophageal reflux disease and Barrett’s esophagus were grouped and reported with dyspepsia

The following Adverse Reactions occurred in patients with an overall frequency of < 2% and are listed in descending order within each System Organ Class:

Cardiac disorders: palpitations, tachycardia, bradycardia, extrasystoles

Ear and labyrinth disorders: vertigo, tinnitus

Endocrine disorders: hypogonadism

Eye disorders: vision blurred, diplopia, dry eye, miosis

Gastrointestinal disorders: flatulence, dysphagia, hematochezia, abdominal distension, hemorrhoids, abnormal feces, intestinal obstruction, eructation, diverticulum, gastrointestinal motility disorder, large intestine perforation, anal fissure, bezoar, duodenitis, ileus, impaired gastric emptying, painful defecation

General disorders and administration site conditions: chills, malaise, feeling abnormal, feeling of body temperature change, feeling jittery, hangover, gait disturbance, feeling drunk, body temperature decreased

Infections and infestations: gastroenteritis, diverticulitis

Injury, poisoning and procedural complications: contusion, overdose

Investigations: weight decreased, hepatic enzyme increased, blood potassium decreased, blood amylase increased, blood testosterone decreased

Metabolism and nutrition disorders: dehydration, fluid retention, increased appetite, hyperuricemia

Musculoskeletal and connective tissue disorders: myalgia

Nervous system disorders: tremor, sedation, hypoesthesia, paresthesia, disturbance in attention, memory impairment, dysarthria, syncope, balance disorder, dysgeusia, depressed level of consciousness, coordination abnormal, hyperesthesia, myoclonus, dyskinesia, crying, hyperreflexia, encephalopathy, cognitive disorder, convulsion, psychomotor hyperactivity

Psychiatric disorders: confusional state, nervousness, restlessness, abnormal dreams, mood altered, hallucination, panic attack, euphoric mood, paranoia, dysphoria, listless, suicide ideation, libido decreased, aggression

Renal and urinary disorders: dysuria, urinary retention, urinary frequency, urinary hesitation, micturition disorder

Reproductive system and breast disorders: erectile dysfunction, sexual dysfunction

Respiratory, thoracic and mediastinal disorders: rhinorrhea, respiratory distress, hypoxia, bronchospasm, sneezing, hyperventilation, respiratory depression

Skin and subcutaneous tissue disorders: erythema

Vascular disorders: flushing, hypertension, hypotension

6.2 Postmarketing Experience

The following adverse reactions have been identified during post approval use of hydromorphone. Because these reactions are reported voluntarily from a population of uncertain size, it is not always possible to reliably estimate their frequency or establish a causal relationship to drug exposure.

Serotonin syndrome: Cases of serotonin syndrome, a potentially life-threatening condition, have been reported during concomitant use of opioids with serotonergic drugs [see Drug Interactions (7)].

Adrenal insufficiency: Cases of adrenal insufficiency have been reported with opioid use, more often following greater than one month of use [see Warnings and Precautions (5.8)].

Anaphylaxis: Anaphylactic reaction has been reported with ingredients contained in hydromorphone hydrochloride extended-release tablets [see Contraindications (4) and Warnings and Precautions (5.14)].

Androgen deficiency: Cases of androgen deficiency have occurred with use of opioids for an extended period of time [see Clinical Pharmacology (12.2)].

Hyperalgesia and Allodynia: Cases of hyperalgesia and allodynia have been reported with opioid therapy of any duration [see Warnings and Precautions (5.6)].

Hypoglycemia: Cases of hypoglycemia have been reported in patients taking opioids. Most reports were in patients with at least one predisposing risk factor (e.g., diabetes).

Opioid-induced esophageal dysfunction (OIED): Cases of OIED have been reported in patients taking opioids, and may occur more frequently in patients taking higher doses of opioids, and/or in patients taking opioids longer term [see Warnings and Precautions (5.11)].

Adverse Reactions from Observational Studies

A prospective, observational cohort study estimated the risks of addiction, abuse, and misuse in patients initiating long-term use of Schedule II opioid analgesics between 2017 and 2021. Study participants included in one or more analyses had been enrolled in selected insurance plans or health systems for at least one year, were free of at least one outcome at baseline, completed a minimum number of follow-up assessments, and either: 1) filled multiple extended-release/long-acting opioid analgesic prescriptions during a 90 day period (n=978); or 2) filled any Schedule II opioid analgesic prescriptions covering at least 70 of 90 days (n=1,244). Those included also had no dispensing of the qualifying opioids in the previous 6 months.

Over 12 months:

- Approximately 1% to 6% of participants across the two cohorts newly met criteria for addiction, as assessed with two validated interview-based measures of moderate-to-severe opioid use disorder based on Diagnostic and Statistical Manual of Mental Disorders, Fifth Edition (DSM-5) criteria, and
- Approximately 9% and 22% of participants across the two cohorts newly met criteria for prescription opioid abuse and misuse [defined in Drug Abuse and Dependence (9.2)], respectively, as measured with a validated self-reported instrument.

A retrospective, observational cohort study estimated the risk of opioid-involved overdose or opioid overdose-related death in patients with new long-term use of Schedule II opioid analgesics from 2006 through 2016 (n=220,249). Included patients had been enrolled in either one of two commercial insurance programs, one managed care program, or one Medicaid program for at least 9 months. New Long-term use was defined as having Schedule II opioid analgesic prescriptions covering at least 70 days’ supply over the 3 months prior to study entry and none during the preceding 6 months. Patients were excluded if they had an opioid-involved overdose in the 9 months prior to study entry. Overdose was measured using a validated medical code-based algorithm with linkage to the National Death Index database. The 5-year cumulative incidence estimates for opioid-involved overdose or opioid overdose-related death ranged from approximately 1.5% to 4% across study sites, counting only the first event during follow-up. Approximately 17% of first opioid overdoses observed over the entire study period (5-11 years, depending on the study site) were fatal. Higher baseline opioid dose was the strongest and most consistent predictor of opioid-involved overdose or opioid overdose-related death. Study exclusion criteria may have selected patients at lower risk of overdose, and substantial loss to follow-up (approximately 80%) also may have biased estimates.

The risk estimates from the studies described above may not be generalizable to all patients receiving opioid analgesics, such as those with exposures shorter or longer than the duration evaluated in the studies.

7 DRUG INTERACTIONS

Table 4 includes clinically significant drug interactions with hydromorphone hydrochloride extended-release tablets.

Table 4.

Clinically Significant Drug Interactions with hydromorphone hydrochloride extended-release tablets

Benzodiazepines and Other Central Nervous System (CNS) Depressants
Clinical Impact: | Due to additive pharmacologic effect, the concomitant use of benzodiazepines or other CNS depressants, including alcohol, can increase the risk of hypotension, respiratory depression, profound sedation, coma, and death.
Intervention: | Reserve concomitant prescribing of these drugs for use in patients for whom alternative treatment options are inadequate. Limit dosages and durations to the minimum required. Inform patients and caregivers of this potential interaction, educate them on the signs and symptoms of respiratory depression (including sedation). If concomitant use is warranted, consider recommending or prescribing an opioid overdose reversal agent. Evaluate for signs of opioid withdrawal [see Dosage and Administration (2.2), Warnings and Precautions (5.1, 5.2, 5.3)].
Examples: | Benzodiazepines and other sedatives/hypnotics, anxiolytics, tranquilizers, muscle relaxants, general anesthetics, antipsychotics, gabapentinoids [gabapentin or pregabalin], other opioids, alcohol.
Serotonergic Drugs
Clinical Impact: | The concomitant use of opioids with other drugs that affect the serotonergic neurotransmitter system has resulted in serotonin syndrome.
Intervention: | If concomitant use is warranted, frequently evaluate the patient, particularly during treatment initiation and dose adjustment. Discontinue hydromorphone hydrochloride extended-release tablets if serotonin syndrome is suspected. Evaluate for signs of opioid withdrawal.
Examples: | Selective serotonin reuptake inhibitors (SSRIs), serotonin and norepinephrine reuptake inhibitors (SNRIs), tricyclic antidepressants (TCAs), triptans, 5-HT3 receptor antagonists, drugs that affect the serotonin neurotransmitter system (e.g., mirtazapine, trazodone, tramadol), certain muscle relaxants (i.e., cyclobenzaprine, metaxalone), monoamine oxidase (MAO) inhibitors (those intended to treat psychiatric disorders and also others, such as linezolid and intravenous methylene blue).
Monoamine Oxidase Inhibitors (MAOIs)
Clinical Impact: | MAOI interactions with opioids may manifest as serotonin syndrome or opioid toxicity (e.g., respiratory depression, coma) [see Warnings and Precautions (5.3)].
Intervention: | The use of hydromorphone hydrochloride extended-release tablets is not recommended for patients taking MAOIs or within 14 days of stopping such treatment. Evaluate for signs of opioid withdrawal.
Examples: | phenelzine, tranylcypromine, linezolid
Mixed Agonist/Antagonist and Partial Agonist Opioid Analgesics
Clinical Impact: | May reduce the analgesic effect of hydromorphone hydrochloride extended-release tablets and/or precipitate withdrawal symptoms [see Warnings and Precautions (5.13)].
Intervention: | Avoid concomitant use.
Examples: | butorphanol, nalbuphine, pentazocine, buprenorphine
Muscle Relaxants
Clinical Impact: | Hydromorphone may enhance the neuromuscular blocking action of skeletal muscle relaxants and produce an increased degree of respiratory depression [see Warnings and Precautions (5.3)].
Intervention: | Because respiratory depression may be greater than otherwise expected, decrease the dosage of hydromorphone hydrochloride extended-release tablets and/or the muscle relaxant as necessary. Due to the risk of respiratory depression with concomitant use of skeletal muscle relaxants and opioids, consider recommending or prescribing an opioid overdose reversal agent. Evaluate for signs of opioid withdrawal [see Dosage and Administration (2.2), Warnings and Precautions (5.2, 5.3)].
Examples: | cyclobenzaprine, metaxalone
Diuretics
Clinical Impact: | Opioids can reduce the efficacy of diuretics by inducing the release of antidiuretic hormone.
Intervention: | Evaluate patients for signs of diminished diuresis and/or effects on blood pressure and increase the dosage of the diuretic as needed.
Anticholinergic Drugs
Clinical Impact: | The concomitant use of anticholinergic drugs may increase risk of urinary retention and/or severe constipation, which may lead to paralytic ileus.
Intervention: | Evaluate patients for signs of urinary retention or reduced gastric motility when hydromorphone hydrochloride extended-release tablets is used concomitantly with anticholinergic drugs.

8 USE IN SPECIFIC POPULATIONS

8.1 Pregnancy

Risk Summary

Use of opioid analgesics for an extended period of time during pregnancy may cause neonatal opioid withdrawal syndrome [see Warnings and Precautions (5.4)]. There are no adequate and well-controlled studies in pregnant women. Based on animal data, advise pregnant women of the potential risk to a fetus.

In animal reproduction studies, reduced postnatal survival of pups, developmental delays, and altered behavioral responses were noted following oral treatment of pregnant rats with hydromorphone during gestation and through lactation at doses 2.1 times the human daily dose of 32 mg/day (HDD), respectively. In published studies, neural tube defects were noted following subcutaneous injection of hydromorphone to pregnant hamsters at doses 4.8 times the HDD and soft tissue and skeletal abnormalities were noted following subcutaneous continuous infusion of 2.3 times the HDD to pregnant mice. No malformations were noted at 2.1 or 17 times the HDD in pregnant rats or rabbits, respectively [see Data]. Based on animal data, advise pregnant women of the potential risk to a fetus.

The estimated background risk of major birth defects and miscarriage for the indicated population is unknown. All pregnancies have a background risk of birth defect, loss, or other adverse outcomes. In the U.S. general population, the estimated background risk of major birth defects and miscarriage in clinically recognized pregnancies is 2 to 4% and 15 to 20%, respectively.

Clinical Considerations

Fetal/Neonatal Adverse Reactions

Use of opioid analgesics for an extended period of time during pregnancy for medical or nonmedical purposes can result in physical dependence in the neonate and neonatal opioid withdrawal syndrome shortly after birth. Neonatal opioid withdrawal syndrome presents as irritability, hyperactivity and abnormal sleep pattern, high pitched cry, tremor, vomiting, diarrhea, and failure to gain weight. The onset, duration, and severity of neonatal opioid withdrawal syndrome vary based on the specific opioid used, duration of use, timing and amount of last maternal use, and rate of elimination of the drug by the newborn. Observe newborns for symptoms of neonatal opioid withdrawal syndrome, and manage accordingly [see Warnings and Precautions (5.4)].

Labor or Delivery

Opioids cross the placenta and may produce respiratory depression and psycho-physiologic effects in neonates. An opioid overdose reversal agent, such as naloxone or nalmefene, must be available for reversal of opioid-induced respiratory depression in the neonate. Hydromorphone hydrochloride extended-release tablets is not recommended for use in pregnant women during or immediately prior to labor, when use of shorter-acting analgesics or other analgesic techniques are more appropriate. Opioid analgesics, including hydromorphone hydrochloride extended-release tablets can prolong labor through actions which temporarily reduce the strength, duration, and frequency of uterine contractions. However, this effect is not consistent and may be offset by an increased rate of cervical dilation, which tends to shorten labor. Monitor neonates exposed to opioid analgesics during labor for signs of excess sedation and respiratory depression.

Data

Animal Data

Pregnant rats were treated with hydromorphone hydrochloride from Gestation Day 6 to 17 via oral gavage doses of 1.75, 3.5, or 7 mg/kg/day (0.5, 1.1, or 2.1 times the HDD of 32 mg/day based on body surface area, respectively). Maternal toxicity was noted in all treatment groups (reduced food consumption and body weights in the two highest dose groups). There was no evidence of malformations or embryotoxicity reported.

Pregnant rabbits were treated with hydromorphone hydrochloride from Gestation Day 6 to 20 via oral gavage doses of 10, 25, or 50 mg/kg/day (4.3, 8.5, or 17 times the HDD of 32 mg/day based on body surface area, respectively). Maternal toxicity was noted in the highest dose group (reduced food consumption and body weights). There was no evidence of malformations or embryotoxicity reported.

In a published study, neural tube defects (exencephaly and cranioschisis) were noted following subcutaneous administration of hydromorphone hydrochloride (19 to 258 mg/kg) on Gestation Day 8 to pregnant hamsters (4.8 to 65.4 times the HDD of 32 mg/day based on body surface area). The findings cannot be clearly attributed to maternal toxicity. No neural tube defects were noted at 14 mg/kg (3.5 times the human daily dose of 32 mg/day). In a published study, CF-1 mice were treated subcutaneously with continuous infusion of 7.5, 15, or 30 mg/kg/day hydromorphone hydrochloride (1.1, 2.3, or 4.6 times the human daily dose of 32 mg based on body surface area) via implanted osmotic pumps during organogenesis (Gestation Days 7 to 10). Soft tissue malformations (cryptorchidism, cleft palate, malformed ventricles and retina), and skeletal variations (split supraoccipital, checkerboard and split sternebrae, delayed ossification of the paws and ectopic ossification sites) were observed at doses 2.3 times the human dose of 32 mg/day based on body surface area. The findings cannot be clearly attributed to maternal toxicity.

Pregnant rats were treated with hydromorphone hydrochloride from Gestation Day 6 to Lactation Day 21 via oral gavage doses of 1.75, 3.5, or 7 mg/kg/day (0.5, 1.1, or 2.1 times the HDD of 32 mg/day based on body surface area, respectively). Reduced pup weights were noted at 1.1 and 2.1 times the human daily dose of 32 mg/day and increased pup deaths, delayed ear opening, reduced auditory startle reflex, and reduced open-field activity were also noted at 2.1 times the HDD. Maternal toxicity was noted in all treatment groups (reduced food consumption and body weights in all groups) and decreased maternal care in the high dose group.

8.2 Lactation

Risk Summary

Because of the potential for serious adverse reactions, including excess sedation and respiratory depression in a breastfed infant, advise patients that breastfeeding is not recommended during treatment with hydromorphone hydrochloride extended-release tablets. Low concentrations of hydromorphone have been detected in human milk in clinical trials. Withdrawal symptoms can occur in breastfeeding infants when maternal administration of an opioid analgesic is stopped. Nursing should not be undertaken while a patient is receiving hydromorphone hydrochloride extended-release tablets since hydromorphone is excreted in the milk.

Clinical Considerations

Monitor infants exposed to hydromorphone hydrochloride extended-release tablets through breast milk for excess sedation and respiratory depression. Withdrawal symptoms can occur in breastfed infants when maternal administration of an opioid analgesic is stopped, or when breast-feeding is stopped.

8.3 Females and Males of Reproductive Potential

Infertility

Use of opioids for an extended period of time may cause reduced fertility in females and males of reproductive potential. It is not known whether these effects on fertility are reversible [see Adverse Reactions (6.2), Nonclinical Toxicology (13.1)].

8.4 Pediatric Use

The safety and effectiveness of hydromorphone hydrochloride extended-release tablets in patients 17 years of age and younger have not been established.

8.5 Geriatric Use

Elderly patients (aged 65 years or older) may have increased sensitivity to hydromorphone. In general, use caution when selecting a dosage for an elderly patient, usually starting at the low end of the dosing range, reflecting the greater frequency of decreased hepatic, renal, or cardiac function and of concomitant disease or other drug therapy.

Respiratory depression is the chief risk for elderly patients treated with opioids and has occurred after large initial doses were administered to patients who were not opioid-tolerant or when opioids were co-administered with other agents that depress respiration. Titrate the dosage of hydromorphone hydrochloride extended-release tablets slowly in geriatric patients and frequently reevaluate the patient for signs of central nervous system and respiratory depression [see Warnings and Precautions (5.2)].

Hydromorphone is known to be substantially excreted by the kidney, and the risk of adverse reactions to this drug may be greater in patients with impaired renal function. Because elderly patients are more likely to have decreased renal function, care should be taken in dose selection, and it may be useful to regularly evaluate renal function.

8.6 Hepatic Impairment

In a study that used a single 4 mg oral dose of immediate-release hydromorphone tablets, four-fold increases in plasma levels of hydromorphone (Cmax and AUC0-∞) were observed in patients with moderate hepatic impairment (Child-Pugh Group B). Start patients with moderate hepatic impairment on 25% of the hydromorphone hydrochloride extended-release tablets dose that would be used in patients with normal hepatic function. Closely monitor patients with moderate hepatic impairment for respiratory and central nervous system depression during initiation of therapy with hydromorphone hydrochloride extended-release tablets and during dose titration. The pharmacokinetics of hydromorphone in severe hepatic impairment patients have not been studied. As further increases in Cmax and AUC0-∞ of hydromorphone in this group are expected, use of alternate analgesics is recommended [see Dosage and Administration (2.6)].

8.7 Renal Impairment

Administration of a single 4 mg dose of immediate-release hydromorphone tablets resulted in two-fold and four-fold increases in plasma levels of hydromorphone (Cmax and AUC0-48h) in moderate (CLcr = 40 to 60 mL/min) and severe (CLcr < 30 mL/min) impairment, respectively. In addition, in patients with severe renal impairment hydromorphone appeared to be more slowly eliminated with longer terminal elimination half-life. Start patients with moderate renal impairment on 50% and patients with severe renal impairment on 25% of the hydromorphone hydrochloride extended-release tablets dose that would be prescribed for patients with normal renal function. Closely monitor patients with renal impairment for respiratory and central nervous system depression during initiation of therapy with hydromorphone hydrochloride extended-release tablets and during dose titration. As hydromorphone hydrochloride extended-release tablets are only intended for once daily administration, consider use of an alternate analgesic that may permit more flexibility with the dosing interval in patients with severe renal impairment [see Dosage and Administration (2.7)].

9 DRUG ABUSE AND DEPENDENCE

9.1 Controlled Substance

Hydromorphone hydrochloride extended-release tablets contain hydromorphone, a Schedule II controlled substance.

9.2 Abuse

Hydromorphone hydrochloride extended-release tablets contain hydromorphone, a substance with a high potential for misuse and abuse, which can lead to the development of substance use disorder, including addiction [see Warnings and Precautions (5.1)].

Misuse is the intentional use, for therapeutic purposes, of a drug by an individual in a way other than prescribed by a health care provider or for whom it was not prescribed.

Abuse is the intentional, non-therapeutic use of a drug, even once, for its desirable psychological or physiological effects.

Drug addiction is a cluster of behavioral, cognitive, and physiological phenomena that may include a strong desire to take the drug, difficulties in controlling drug use (e.g., continuing drug use despite harmful consequences, giving a higher priority to drug use than other activities and obligations), and possible tolerance or physical dependence.

Misuse and abuse of hydromorphone hydrochloride extended-release tablets increases risk of overdose, which may lead to central nervous system and respiratory depression, hypotension, seizures, and death. The risk is increased with concurrent abuse of hydromorphone hydrochloride extended-release tablets with alcohol and other central nervous system depressants. Abuse of and addiction to opioids in some individuals may not be accompanied by concurrent tolerance and symptoms of physical dependence. In addition, abuse of opioids can occur in the absence of addiction.

All patients treated with opioids require careful and frequent re-evaluation for signs of misuse, abuse, and addiction, because use of opioid analgesic products carries the risk of addiction even under appropriate medical use. Patients at high risk of hydromorphone hydrochloride extended-release tablets abuse include those with a history of prolonged use of any opioid, including products containing hydromorphone, those with a history of drug or alcohol abuse, or those who use hydromorphone hydrochloride extended-release tablets in combination with other abused drugs.

“Drug-seeking” behavior is very common in persons with substance use disorders. Drug-seeking tactics include emergency calls or visits near the end of office hours, refusal to undergo appropriate examination, testing, or referral, repeated “loss” of prescriptions, tampering with prescriptions, and reluctance to provide prior medical records or contact information for other treating healthcare provider(s). “Doctor shopping” (visiting multiple prescribers to obtain additional prescriptions) is common among people who abuse drugs and people with substance use disorder. Preoccupation with achieving adequate pain relief can be appropriate behavior in a patient with inadequate pain control.

Hydromorphone hydrochloride extended-release tablets, like other opioids, can be diverted for non-medical use into illicit channels of distribution. Careful record-keeping of prescribing information, including quantity, frequency, and renewal requests, as required by state and federal law, is strongly advised.

Proper assessment of the patient, proper prescribing practices, periodic reevaluation of therapy, and proper dispensing and storage are appropriate measures that help to limit abuse of opioid drugs.

Risks Specific to Abuse of Hydromorphone Hydrochloride Extended-Release Tablets

Abuse of hydromorphone hydrochloride extended-release tablets poses a risk of overdose and death. The risk is increased with concurrent use of hydromorphone hydrochloride extended-release tablets with alcohol and/or other central nervous system depressants. Taking cut, broken, chewed, crushed, or dissolved hydromorphone hydrochloride extended-release tablets enhances drug release and increases the risk of overdose and death.

Hydromorphone hydrochloride extended-release tablets are approved for oral use only. Inappropriate intravenous, intramuscular, or subcutaneous use of hydromorphone hydrochloride extended-release tablets can result in death, local tissue necrosis, infection, pulmonary granulomas, increased risk of endocarditis, and valvular heart injury, and embolism.

Parenteral drug abuse is commonly associated with transmission of infectious diseases such as hepatitis and HIV.

9.3 Dependence

Both tolerance and physical dependence can develop during use of opioid therapy.

Tolerance is a physiological state characterized by a reduced response to a drug after repeated administration (i.e., a higher dose of a drug is required to produce the same effect that was once obtained at a lower dose).

Physical dependence is a state that develops as a result of a physiological adaptation in response to repeated drug use, manifested by withdrawal signs and symptoms after abrupt discontinuation or a significant dose reduction of a drug.

Withdrawal may be precipitated through the administration of drugs with opioid antagonist activity (e.g., naloxone, nalmefene), mixed agonist/antagonist analgesics (e.g., pentazocine, butorphanol, nalbuphine), or partial agonists

(e.g., buprenorphine). Physical dependence may not occur to a clinically significant degree until after several days to weeks of continued use.

Do not rapidly reduce or abruptly discontinue hydromorphone hydrochloride extended-release tablets in a patient physically dependent on opioids. Rapid reduction or abrupt discontinuation of hydromorphone hydrochloride extended-release tablets in a patient physically dependent on opioids may lead to serious withdrawal symptoms, uncontrolled pain, and suicide. Rapid reduction or abrupt discontinuation has also been associated with attempts to find other sources of opioid analgesics, which may be confused with drug-seeking for abuse.

When discontinuing hydromorphone hydrochloride extended-release tablets, gradually taper the dosage using a patient-specific plan that considers the following: the dose of hydromorphone hydrochloride extended-release tablets the patient has been taking, the duration of treatment, and the physical and psychological attributes of the patient. To improve the likelihood of a successful taper and minimize withdrawal symptoms, it is important that the opioid tapering schedule is agreed upon by the patient. In patients taking opioids for an extended period of time at high doses, ensure that a multimodal approach to pain management, including mental health support (if needed), is in place prior to initiating an opioid analgesic taper [see Dosage and Administration (2.1), and Warnings and Precautions (5.13)].

Infants born to mothers physically dependent on opioids will also be physically dependent and may exhibit respiratory difficulties and withdrawal signs [see Use in Specific Populations (8.1)].

10 OVERDOSAGE

Clinical Presentation

Acute overdosage with hydromorphone hydrochloride extended-release tablets can be manifested by respiratory depression, somnolence progressing to stupor or coma, skeletal muscle flaccidity, cold and clammy skin, constricted pupils, and, in some cases pulmonary edema, bradycardia, hypotension, hypoglycemia, partial or complete airway obstruction, atypical snoring, and death. Marked mydriasis rather than miosis may be seen with hypoxia in overdose situations [see Clinical Pharmacology (12.2)]. Toxic leukoencephalopathy has been reported after opioid overdose and can present hours, days, or weeks after apparent recovery from the initial intoxication.

Treatment of Overdose

In case of overdose, priorities are the re-establishment of a patent and protected airway and institution of assisted or controlled ventilation, if needed. Employ other supportive measures (including oxygen and vasopressors) in the management of circulatory shock and pulmonary edema as indicated. Cardiac arrest or arrhythmias will require advanced life support measures.

For clinically significant respiratory or circulatory depression secondary to opioid overdose, administer an opioid overdose reversal agent such as naloxone or nalmefene.

Because the duration of reversal is expected to be less than the duration of action of hydromorphone in hydromorphone hydrochloride extended-release tablets, carefully monitor the patient until spontaneous respiration is reliably reestablished. Hydromorphone hydrochloride extended-release tablets will continue to release hydromorphone and add to the hydromorphone load for up to 24 to 48 hours or longer following ingestion, necessitating prolonged monitoring. If the response to an opioid overdose reversal agent is suboptimal or only brief in nature, administer additional reversal agent as directed by the product’s prescribing information.

In an individual physically dependent on opioids, administration of the recommended usual dosage of the opioid overdose reversal agent will precipitate an acute withdrawal syndrome. The severity of the withdrawal symptoms experienced will depend on the degree of physical dependence and the dose of the reversal agent administered. If a decision is made to treat serious respiratory depression in the physically dependent patient, administration of the antagonist should be initiated with care and by titration with smaller than usual doses of the reversal agent.

11 DESCRIPTION

Hydromorphone hydrochloride extended-release tablets are for oral use and contain hydromorphone hydrochloride, an opioid agonist.

Hydromorphone hydrochloride USP is 4,5α-epoxy-3-hydroxy-17-methlymorphinan-6-one hydrochloride. Hydromorphone hydrochloride is a white or almost white crystalline powder that is freely soluble in water, very slightly soluble in ethanol (96%), and practically insoluble in methylene chloride. Its empirical formula is C17H19NO3•HCl. The compound has the following structural formula:

Hydromorphone hydrochloride extended-release tablets also contains the following inactive ingredients: polyethylene glycol, polyethylene oxide, hypromellose, magnesium stearate, sodium chloride, colloidal silicon dioxide, cellulose acetate, black iron oxide, lactose monohydrate, titanium dioxide, triacetin, FD&C red #40 aluminum lake (8 mg and 24 mg), iron oxide yellow (12 mg and 16 mg), D&C yellow #10 aluminum lake (16 mg), FD&C yellow #6 aluminum lake (16 mg and 24 mg), FD&C blue #2 aluminum lake (24 mg).

12 CLINICAL PHARMACOLOGY

12.1 Mechanism of Action

Hydromorphone, a semi-synthetic morphine derivative, is a hydrogenated ketone of morphine. Hydromorphone is a full opioid agonist and is relatively selective for the mu-opioid receptor, although it can bind to other opioid receptors at higher doses. The principal therapeutic action of hydromorphone is analgesia. Like all full opioid agonists, there is no ceiling effect for analgesia with morphine. Clinically, dosage is titrated to provide adequate analgesia and may be limited by adverse reactions, including respiratory and CNS depression.

The precise mechanism of the analgesic action is unknown. However, specific CNS opioid receptors for endogenous compounds with opioid-like activity have been identified throughout the brain and spinal cord and are thought to play a role in the analgesic effects of this drug.

12.2 Pharmacodynamics

CNS Depressant/Alcohol Interaction

Additive pharmacodynamic effects may be expected when hydromorphone hydrochloride extended-release tablets are used in conjunction with alcohol, other opioids, legal or illicit drugs that cause central nervous system depression.

Effects on the Central Nervous System

Hydromorphone produces dose-related respiratory depression by direct action on brain stem respiratory centers. The respiratory depression involves a reduction in the responsiveness of the brain stem respiratory centers to both increases in carbon dioxide tension and to electrical stimulation.

Hydromorphone causes miosis, even in total darkness. Pinpoint pupils are a sign of opioid overdose but are not pathognomic (e.g., pontine lesions of hemorrhagic or ischemic origins may produce similar findings). Marked mydriasis, rather than miosis, may be seen due to severe hypoxia in overdose situations.

Effects on the Gastrointestinal Tract and Other Smooth Muscle

Hydromorphone causes a reduction in motility associated with an increase in tone in the antrum of the stomach and duodenum. Digestion of food in the small intestine is delayed and propulsive contractions are decreased. Propulsive peristaltic waves in the colon are decreased, while tone is increased to the point of spasm, resulting in constipation. Other opioid-induced effects may include a reduction in biliary and pancreatic secretions, spasm of sphincter of Oddi, transient elevations in serum amylase, and opioid-induced esophageal dysfunction (OIED).

Effects on the Cardiovascular System

Hydromorphone produces peripheral vasodilation which may result in orthostatic hypotension or syncope. Release of histamine may be induced by hydromorphone and can contribute to opioid-induced hypotension. Manifestations of histamine release or peripheral vasodilation may include pruritus, flushing, red eyes, sweating, and/or orthostatic hypotension.

Effects on the Endocrine System

Opioids inhibit the secretion of ACTH, cortisol, and luteinizing hormone (LH) in humans. They also stimulate prolactin, growth hormone (GH) secretion, and pancreatic secretion of insulin and glucagon.

Use of opioids for an extended period of time may influence the hypothalamic-pituitary-gonadal axis, leading to androgen deficiency that may manifest as low libido, impotence, erectile dysfunction, amenorrhea, or infertility. The causal role of opioids in the clinical syndrome of hypogonadism is unknown because the various medical, physical, lifestyle, and psychological stressors that may influence gonadal hormone levels have not been adequately controlled for in studies conducted to date [see Adverse Reactions (6.2)].

Effects on the Immune System

Opioids have been shown to have a variety of effects on components of the immune system in in vitro and animal models. The clinical significance of these findings is unknown. Overall, the effects of opioids appear to be modestly immunosuppressive.

Concentration-Efficacy Relationships

The minimum effective analgesic concentration will vary widely among patients, especially among patients who have been previously treated with opioid agonists. The minimum effective analgesic concentration of hydromorphone for any individual patient may increase over time due to an increase in pain, the development of a new pain syndrome, and/or the development of analgesic tolerance [see Dosage and Administration (2.1), (2.4)].

Concentration-Adverse Reaction Relationships

There is a relationship between increasing hydromorphone plasma concentration and increasing frequency of dose-related opioid adverse reactions such as nausea, vomiting, CNS effects, and respiratory depression. In opioid-tolerant patients, the situation may be altered by the development of tolerance to opioid-related adverse reactions [see Dosage and Administration (2.1), (2.3), (2.4)].

12.3 Pharmacokinetics

Absorption

Hydromorphone hydrochloride extended-release tablets are an extended-release formulation of hydromorphone that produces a gradual increase in hydromorphone concentrations. Following a single-dose administration of hydromorphone hydrochloride extended-release tablets, plasma concentrations gradually increase over 6 to 8 hours, and thereafter concentrations are sustained for approximately 18 to 24 hours post-dose. The median Tmax values ranged from 12 to 16 hours. The mean half-life was approximately 11 hours, ranging from 8 to 15 hours in most individual subjects. Linear pharmacokinetics has been demonstrated for hydromorphone hydrochloride extended-release tablets over the dose range 8 to 64 mg, with a dose-proportional increase in Cmax and overall exposure (AUC0-∞) (see Table 5). Steady-state plasma concentrations are approximately twice those observed following the first dose, and steady state is reached after 3 to 4 days of once-daily dosing of hydromorphone hydrochloride extended-release tablets. At steady state, hydromorphone hydrochloride extended-release tablets given once daily maintained hydromorphone plasma concentrations within the same concentration range as the immediate-release tablet given 4 times daily at the same total daily dose and diminished the fluctuations between peak and trough concentrations seen with the immediate-release tablet (see Figure 1). The bioavailability of hydromorphone hydrochloride extended-release tablets once daily and immediate-release hydromorphone four times daily in adults is comparable, as presented in Table 5.

Table 5. Mean (±SD) Hydromorphone Hydrochloride Extended-Release Tablets Pharmacokinetic Parameters

NA = not applicable
*Median (range) reported for Tmax
† Steady-state results on Day 5 (0-24 hours)
‡ Cmin 2.15 (0.87) ng/mL
§ Cmin 1.47 (0.42) ng/mL

Food Effect

The pharmacokinetics of hydromorphone hydrochloride extended-release tablets are not affected by food as indicated by bioequivalence when administered under fed and fasting conditions. Therefore, hydromorphone hydrochloride extended-release tablets may be administered without regard to meals. When a 16 mg dose of hydromorphone hydrochloride extended-release tablets were administered to healthy volunteers immediately following a high-fat meal, the median time to Cmax (Tmax) was minimally affected by the high-fat meal occurring at 16 hours compared to 18 hours while fasting.

Distribution

Following intravenous administration of hydromorphone to healthy volunteers, the mean volume of distribution was 2.9 (±1.3) L/kg, suggesting extensive tissue distribution. The mean extent of binding of hydromorphone to human plasma proteins was determined to be 27% in an in vitro study.

Elimination

Metabolism

After oral administration of an immediate-release formulation, hydromorphone undergoes extensive first-pass metabolism and is metabolized primarily in the liver by glucuronidation to hydromorphone-3-glucuronide, which follows a similar time course to hydromorphone in plasma. Exposure to the glucuronide metabolite is 35 to 40 times higher than exposure to the parent drug. In vitro data suggest that hydromorphone in clinically relevant concentrations has minimal potential to inhibit the activity of human hepatic CYP450 enzymes including CYP1A2, 2C9, 2C19, 2D6, 3A4, and 4A11.

Excretion

Approximately 75% of the administered dose is excreted in urine. Most of the administered hydromorphone dose is excreted as metabolites. Approximately 7% and 1% of the dose are excreted as unchanged hydromorphone in urine and feces, respectively.

Specific Populations

Age: Geriatric Patients

Population PK analysis performed on plasma concentration data from 407 osteoarthritis (OA) patients using hydromorphone hydrochloride extended-release tablets showed an average 11% increase in hydromorphone AUC in the elderly group (65 to 75 years of age) when compared to the younger age group (less than or equal to 65 years of age).

Sex

Females appeared to have approximately 10% higher mean systemic exposure in terms of Cmax and AUC values.

Hepatic Impairment

In a study that used a single 4 mg oral dose of immediate-release hydromorphone tablets, four-fold increases in plasma levels of hydromorphone (Cmax and AUC0-∞) were observed in patients with moderate hepatic impairment (Child-Pugh Group B). Pharmacokinetics of hydromorphone in severe hepatic impairment patients has not been studied. Further increase in Cmax and AUC0-∞ of hydromorphone in this group is expected. Start patients with moderate hepatic impairment on 25% of the usual dose of hydromorphone hydrochloride extended-release tablets and closely monitor for respiratory and central nervous system depression during dose titration. Consider alternate analgesic therapy for patients with severe hepatic impairment [see Dosage and Administration (2.6) and Specific Populations (8.6)].

Renal Impairment

Renal impairment affected the pharmacokinetics of hydromorphone and its metabolites following administration of a single 4 mg dose of immediate-release tablets. The effects of renal impairment on hydromorphone pharmacokinetics were two-fold and four-fold increases in plasma levels of hydromorphone (Cmax and AUC0-48h) in moderate (CLcr = 40 to 60 mL/min) and severe (CLcr < 30 mL/min) impairment, respectively. In addition, in patients with severe renal impairment hydromorphone appeared to be more slowly eliminated with longer terminal elimination half-life (40 hr) compared to subjects with normal renal function (15 hr). Start patients with moderate renal impairment on 50% of the usual hydromorphone hydrochloride extended-release tablets dose for patients with normal renal function and closely monitor for respiratory and central nervous system depression during dose titration. As hydromorphone hydrochloride extended-release tablets are only intended for once-daily administration, consider use of an alternate analgesic that may permit more flexibility with the dosing interval in patients with severe renal impairment [see Dosage and Administration (2.7) and Use in Specific Populations (8.7)].

Drug Interaction Studies

Alcohol Interaction

An in vivo study examined the effect of alcohol (40%, 20%, 4% and 0%) on the bioavailability of a single dose of 16 mg of hydromorphone hydrochloride extended-release tablets in healthy, fasted or fed volunteers. The results showed that the hydromorphone mean AUC0-∞ was 5% higher and 4% lower (not statistically significant) in the fasted and fed groups respectively after co-administration of 240 mL of 40% alcohol. The AUC0-∞ was similarly unaffected in subjects following the co-administration of hydromorphone hydrochloride extended-release tablets and alcohol (240 mL of 20% or 4% alcohol).

The change in geometric mean Cmax with concomitant administration of alcohol and hydromorphone hydrochloride extended-release tablets ranged from an increase of 10% to 31% across all conditions studied. The change in mean Cmax was greater in the fasted group of subjects. Following concomitant administration of 240 mL of 40% alcohol while fasting, the mean Cmax increased by 37% and up to 151% in an individual subject. Following the concomitant administration of 240 mL of 20% alcohol while fasting, the mean Cmax increased by 35% and up to 139% in an individual subject. Following the concomitant administration of 240 mL of 4% alcohol while fasting, the mean Cmax increased by 19% on average and as much as 73% for an individual subject. The range of median Tmax for the fed and fasted treatments with 4%, 20% and 40% alcohol was 12 to 16 hours compared to 16 hours for the 0% alcohol treatments.

13 NONCLINICAL TOXICOLOGY

13.1 Carcinogenesis, Mutagenesis, Impairment of Fertility

Carcinogenesis

Long-term studies to evaluate the carcinogenic potential of hydromorphone hydrochloride were completed in both Han-Wistar rats and Crl:CD1®(ICR) mice. Hydromorphone HCl was administered to Han-Wistar rats (2, 5, and 15 mg/kg/day for males, and 8, 25 and 75 mg/kg/day for females) for 2 years by oral gavage. In female rats, incidences of hibernoma (tumor of brown fat) were increased at 10.5 times the maximum recommended daily exposure based on AUC at the mid dose (2 tumor, 25 mg/kg/day) and 53.7 times the maximum recommended human daily exposure based on AUC at the maximum dose (4 tumors, 75 mg/kg/day). The clinical relevance of this finding to humans has not been established. There was no evidence of carcinogenicity in male rats. The systemic drug exposure (AUC, ng·h/mL) at the 15 mg/kg/day in male rats was 7.6 times greater than the human exposure at a single dose of 32 mg/day of hydromorphone hydrochloride extended-release tablets. There was no evidence of carcinogenic potential in Crl:CD1®(ICR) mice administered hydromorphone HCl at doses up to 15 mg/kg/day for 2 years by oral gavage. The systemic drug exposure (AUC, ng•h/mL) at the 15 mg/kg/day in mice was 1.1 (in males) and 1.2 (in females) times greater than the human exposure at a single dose of 32 mg/day of hydromorphone hydrochloride extended-release tablets.

Mutagenesis

Hydromorphone was not mutagenic in the in vitro bacterial reverse mutation assay (Ames assay). Hydromorphone was not clastogenic in either the in vitro human lymphocyte chromosome aberration assay or the in vivo mouse micronucleus assay.

Impairment of Fertility

Reduced implantation sites and viable fetuses were noted at 2.1 times the human daily dose of 32 mg/day in a study in which female rats were treated orally with 1.75, 3.5, or 7 mg/kg/day hydromorphone hydrochloride (0.7, 1.4, or 2.8 times a human daily dose of 24 mg/day (HDD) based on body surface area) beginning 14 days prior to mating through Gestation Day 7 and male rats were treated with the same hydromorphone hydrochloride doses beginning 28 days prior to and throughout mating.

14 CLINICAL STUDIES

Hydromorphone hydrochloride extended-release tablets were investigated in a double-blind, placebo-controlled, randomized withdrawal study in opioid tolerant patients with moderate-to-severe low back pain. Patients were considered opioid tolerant if they were currently on opioid therapy that was ≥ 60 mg/day of oral morphine equivalent for at least 2 months prior to screening. Patients entered an open-label conversion and titration phase with hydromorphone hydrochloride extended-release tablets, were converted to a starting dose that was approximately 75% of their total daily morphine equivalent dose, and were dosed once daily until adequate pain control was achieved while exhibiting tolerable side effects. Supplemental immediate-release hydromorphone tablets were allowed throughout the study. Patients who achieved a stable dose entered a 12-week, double-blind, placebo-controlled, randomized treatment phase. Mean daily dose at randomization was 37.8 mg/day (range of 12 mg/day to 64 mg/day). Fifty-eight (58) percent of patients were successfully titrated to a stable dose of hydromorphone hydrochloride extended-release tablets during the open-label conversion and titration phase.

During the double-blind treatment phase, patients randomized to hydromorphone hydrochloride extended-release tablets continued with the stable dose achieved in the conversion and titration phase of the study. Patients randomized to placebo received, in a blinded manner, hydromorphone hydrochloride extended-release tablets and matching placebo in doses tapering from the stable dose achieved in conversion and titration. During the taper down period, patients were allowed immediate-release hydromorphone tablets as supplemental analgesia to minimize opioid withdrawal symptoms in placebo patients. After the taper period, the number of immediate-release hydromorphone tablets was limited to two tablets per day. Forty-nine (49) percent of patients treated with hydromorphone hydrochloride extended-release tablets and 33% of patients treated with placebo completed the 12-week treatment period.

Hydromorphone hydrochloride extended-release tablets provided superior analgesia compared to placebo. There was a significant difference between the mean changes from Baseline to Week 12 or Final Visit in average weekly pain intensity Numeric Rating Scale (NRS) scores obtained from patient diaries between the two groups. The proportion of patients with various degrees of improvement from screening to Week 12 or Final Visit is shown in Figure 2. For this analysis, patients who discontinued treatment for any reason prior to Week 12 were assigned a value of zero improvement.

16 HOW SUPPLIED/STORAGE AND HANDLING

How Supplied

Hydromorphone Hydrochloride Extended-Release Tablets Strengths

Strength | Color | Tablet Description | Packaging | NDC
8 mg | Pink | Round, biconvex, printed with "OS 211" | 100 tablets per bottle | 13811-701-10
12 mg | Dark Yellow | Round, biconvex, printed with "OS 212" | 100 tablets per bottle | 13811-702-10
16 mg | Yellow | Round, biconvex, printed with "OS 213" | 100 tablets per bottle | 13811-703-10
24 mg | Gray | Round, biconvex, printed with "OS 216" | 100 tablets per bottle | 13811-720-10
32 mg | White | Round, biconvex, printed with "OS 214" | 100 tablets per bottle | 13811-704-10

Store at 25ºC (77ºF); excursions permitted to 15° to 30° C (59° to 86° F) [See USP Controlled Room Temperature].

17 PATIENT COUNSELING INFORMATION

Advise the patient to read the FDA-approved patient labeling (Medication Guide).

Storage and Disposal

Because of the risks associated with accidental ingestion, misuse, and abuse, advise patients to store hydromorphone hydrochloride extended-release tablets securely, out of sight and reach of children, and in a location not accessible by others, including visitors to the home. Inform patients that leaving hydromorphone hydrochloride extended-release tablets unsecured can pose a deadly risk to others in the home [see Warnings and Precautions (5.1, 5.5), Drug Abuse and Dependence (9.2)].

Advise patients and caregivers that when medicines are no longer needed, they should be disposed of promptly. Expired, unwanted, or unused hydromorphone hydrochloride extended-release tablets should be disposed of by flushing the unused medication down the toilet if a drug take-back option is not readily available. Inform patients that they can visit www.fda.gov/drugdisposal for a complete list of medicines recommended for disposal by flushing, as well as additional information on disposal of unused medicines.

Addiction, Abuse, and Misuse

Inform patients that the use of hydromorphone hydrochloride extended-release tablets, even when taken as recommended, can result in addiction, abuse, and misuse, which can lead to overdose or death [see Warnings and Precautions (5.1)]. Instruct patients not to share hydromorphone hydrochloride extended-release tablets with others and to take steps to protect hydromorphone hydrochloride extended-release tablets from theft or misuse.

Life-Threatening Respiratory Depression

Inform patients of the risk of life-threatening respiratory depression, including information that the risk is greatest when starting hydromorphone hydrochloride extended-release tablets or when the dose is increased, and that it can occur even at recommended dosages.

Educate patients and caregivers on how to recognize respiratory depression and emphasize the importance of calling 911 or getting emergency medical help right away in the event of a known or suspected overdose [see Warnings and Precautions (5.2)].

Accidental Ingestion

Inform patients that accidental ingestion, especially by children, may result in respiratory depression or death [see Warnings and Precautions (5.2)].

Interactions with Benzodiazepines and Other CNS Depressants

Inform patients and caregivers that potentially fatal additive effects may occur if hydromorphone hydrochloride extended-release tablets are used with benzodiazepines or other CNS depressants, including alcohol (e.g., non-benzodiazepine sedative/hypnotics, anxiolytics, tranquilizers, muscle relaxants, general anesthetics, antipsychotics, gabapentinoids [gabapentin or pregabalin], and other opioids), and not to use these concomitantly unless supervised by a health care provider [see Warnings and Precautions (5.3), Drug Interactions (7)].

Patient Access to an Opioid Overdose Reversal Agent for the Emergency Treatment of Opioid Overdose

Inform patients and caregivers about opioid overdose reversal agents (e.g., naloxone, nalmefene). Discuss the importance of having access to an opioid overdose reversal agent, especially if the patient has risk factors for overdose (e.g., concomitant use of CNS depressants, a history of opioid use disorder, or prior opioid overdose) or if there are household members (including children) or other close contacts at risk for accidental ingestion or opioid overdose.

Discuss with the patient the options for obtaining an opioid overdose reversal agent (e.g., prescription, over-the-counter, or as part of a community-based program) [see Dosage and Administration (2.2), Warnings and Precautions (5.3)].

Educate patients and caregivers on how to recognize the signs and symptoms of an overdose.

Explain to patients and caregivers that effects of opioid overdose reversal agents like naloxone and nalmefene are temporary, and that they must call 911 or get emergency medical help right away in all cases of known or suspected opioid overdose, even if an opioid overdose reversal agent is administered [see Overdosage (10)].

Advise patients and caregivers:

- how to treat with the overdose reversal agent in the event of an opioid overdose
- to tell family and friends about the opioid overdose reversal agent, and to keep it in a place where family and friends can access it in an emergency
- to read the Patient Information (or other educational material) that will come with their opioid overdose reversal agent. Emphasize the importance of doing this before an opioid emergency happens, so the patient and caregiver will know what to do

Hyperalgesia and Allodynia

Inform patients and caregivers not to increase opioid dosage without first consulting a clinician. Advise patients to seek medical attention if they experience symptoms of hyperalgesia, including worsening pain, increased sensitivity to pain, or new pain [see Warnings and Precautions (5.6); Adverse Reactions (6.2)].

Serotonin Syndrome

Inform patients that hydromorphone hydrochloride extended-release tablets could cause a rare but potentially life-threatening condition resulting from concomitant administration of serotonergic drugs. Warn patients of the symptoms of serotonin syndrome and to seek medical attention right away if symptoms develop. Instruct patients to inform their healthcare providers if they are taking, or plan to take serotonergic medications [see Drug Interactions (7)].

MAOI Interaction

Inform patients to avoid taking hydromorphone hydrochloride extended-release tablets while using any drugs that inhibit monoamine oxidase. Patients should not start MAOIs while taking hydromorphone hydrochloride extended-release tablets [see Drug Interactions (7)].

Important Administration Instructions

Instruct patients how to properly take hydromorphone hydrochloride extended-release tablets, including the following:

- Hydromorphone Hydrochloride extended-release tablets are designed to work properly only if swallowed intact. Taking cut, broken, chewed, crushed, or dissolved hydromorphone hydrochloride extended-release tablets can result in a fatal overdose [see Dosage and Administration (2.1)].
- Using hydromorphone hydrochloride extended-release tablets exactly as prescribed to reduce the risk of life-threatening adverse reactions (e.g., respiratory depression).

Important Discontinuation Instructions

In order to avoid developing withdrawal symptoms, instruct patients not to discontinue hydromorphone hydrochloride extended-release tablets without first discussing a tapering plan with the prescriber [see Dosage and Administration (2.5)].

Driving or Operating Heavy Machinery

Inform patients that hydromorphone hydrochloride extended-release tablets may impair the ability to perform potentially hazardous activities such as driving a car or operating heavy machinery. Advise patients not to perform such tasks until they know how they will react to the medication [see Warnings and Precautions (5.15)].

Constipation

Advise patients of the potential for severe constipation, including management instructions and when to seek medical attention [see Adverse Reactions (6.1), Clinical Pharmacology (12.2)].

Adrenal Insufficiency

Inform patients that hydromorphone hydrochloride extended-release tablets could cause adrenal insufficiency, a potentially life-threatening condition. Adrenal insufficiency may present with non-specific symptoms and signs such as nausea, vomiting, anorexia, fatigue, weakness, dizziness, and low blood pressure. Advise patients to seek medical attention if they experience a constellation of these symptoms [see Warnings and Precautions (5.8)].

Gastrointestinal Blockage

Advise patients that people with certain stomach or intestinal problems such as narrowing of the intestines or previous surgery may be at higher risk of developing a blockage. Symptoms include abdominal distension, abdominal pain, severe constipation, or vomiting. Instruct patients to contact their healthcare provider immediately if they develop these symptoms.

Hypotension

Inform patients that hydromorphone hydrochloride extended-release tablets may cause orthostatic hypotension and syncope. Instruct patients how to recognize symptoms of low blood pressure and how to reduce the risk of serious consequences should hypotension occur (e.g., sit or lie down, carefully rise from a sitting or lying position).

Anaphylaxis

Inform patients that anaphylaxis has been reported with ingredients contained in hydromorphone hydrochloride extended-release tablets. Advise patients how to recognize such a reaction and when to seek medical attention [see Contraindications (4), Warnings and Precautions (5.14), and Adverse Reactions (6.2)].

Pregnancy

Neonatal Opioid Withdrawal Syndrome

Inform female patients of reproductive potential that use of hydromorphone hydrochloride extended-release tablets for an extended period of time during pregnancy can result in neonatal opioid withdrawal syndrome, which may be life-threatening if not recognized and treated [see Warnings and Precautions (5.4), Use in Specific Populations (8.1)].

Embryo-Fetal Toxicity

Inform female patients of reproductive potential that hydromorphone hydrochloride extended-release tablets can cause fetal harm and to inform their healthcare provider of a known or suspected pregnancy [see Use in Specific Populations (8.1)].

Lactation

Advise patients that breastfeeding is not recommended during treatment with hydromorphone hydrochloride extended-release tablets [see Use in Specific Populations (8.2)].

Infertility

Inform patients that chronic use of opioids for an extended period of time may cause reduced fertility. It is not known whether these effects on fertility are reversible [see Use in Specific Populations (8.3)].

Manufactured for:

Trigen Laboratories, LLC

Alpharetta, GA 30005

www.trigenlab.com

200252-09 Rev. 12/2025

Medication Guide

Hydromorphone Hydrochloride Extended-Release Tablets, CII

(hy-druh-mor-fon hy-druh-klawr-ahyd)

Hydromorphone hydrochloride extended-release tablets are:

- A strong prescription pain medicine that contains an opioid (narcotic) that is used to manage severe and persistent pain that requires an extended treatment period with a daily opioid pain medicine, when other pain treatments such as non-opioid pain medicines or immediate-release opioid medicines do not treat your pain well enough or you cannot tolerate them.
- A long-acting (extended-release) opioid pain medicine that can put you at risk for overdose and death. Even if you take your dose correctly as prescribed you are at risk for opioid addiction, abuse, and misuse that can lead to death.
- Not to be taken on an “as needed” basis.

Important information about hydromorphone hydrochloride extended-release tablets:

- Get emergency help or call 911 right away if you take too much hydromorphone hydrochloride extended-release tablets (overdose). When you first start taking hydromorphone hydrochloride extended-release tablets, when your dose is changed, or if you take too much (overdose), serious or life-threatening breathing problems that can lead to death may occur. Ask your healthcare provider about medicines like naloxone or nalmefene that can be used in an emergency to reverse an opioid overdose.
- Taking hydromorphone hydrochloride extended-release tablets with other opioid medicines, benzodiazepines, gabapentinoids (gabapentin or pregabalin), alcohol, or other central nervous system depressants (including street drugs) can cause severe drowsiness, decreased awareness, breathing problems, coma, and death.
- Never give anyone else your hydromorphone hydrochloride extended-release tablets. They could die from taking it. Selling or giving away hydromorphone hydrochloride extended-release tablets is against the law.
- Store hydromorphone hydrochloride extended-release tablets securely, out of sight and reach of children, and in a location not accessible by others, including visitors to the home.

Do not take hydromorphone hydrochloride extended-release tablets if you have:

- severe asthma, trouble breathing, or other lung problems.
- a bowel blockage or have narrowing of the stomach or intestines.

Before taking hydromorphone hydrochloride extended-release tablets, tell your healthcare provider if you have a history of:

- head injury, seizures
- problems urinating
- liver, kidney, thyroid problems
- pancreas or gallbladder problems
- allergy to sulfites
- abuse of street or prescription drugs, alcohol addiction, opioid overdose, or mental health problems.

Tell your healthcare provider if you:

- Notice your pain getting worse. If your pain gets worse after you take hydromorphone hydrochloride extended-release tablets, do not take more of hydromorphone hydrochloride extended-release tablets without first talking to your healthcare provider. Talk to your healthcare provider if the pain that you have increases, if you feel more sensitive to pain, or if you have new pain after taking hydromorphone hydrochloride extended-release tablets.
- Are pregnant or planning to become pregnant. Use of hydromorphone hydrochloride extended-release tablets for an extended period of time during pregnancy can cause withdrawal symptoms in your newborn baby that could be life-threatening if not recognized and treated.
- Are breastfeeding. Not recommended during treatment with hydromorphone hydrochloride extended-release tablets.It may harm your baby.
- Are living in a household where there are small children or someone who has abused street or prescription drugs
- Are taking prescription or over-the-counter medicines, vitamins, or herbal supplements. Taking hydromorphone hydrochloride extended-release tablets with certain other medicines can cause serious side effects.

When taking hydromorphone hydrochloride extended-release tablets:

- Do not change your dose. Take hydromorphone hydrochloride extended-release tablets exactly as prescribed by your healthcare provider. Use the lowest dose possible for the shortest time needed.
- Take your prescribed dose every 24 hours, at the same time every day. Do not take more than your prescribed dose in 24 hours. If you miss a dose, take your next dose at your usual time the next day.
- Swallow hydromorphone hydrochloride extended-release tablets whole. Do not cut, break, chew, crush, dissolve, snort, or inject hydromorphone hydrochloride extended-release tablets because this may cause you to overdose and die.
- Call your healthcare provider if the dose you are taking does not control your pain.
- Do not stop taking hydromorphone hydrochloride extended-release tablets without talking to your healthcare provider.
- Hydromorphone hydrochloride extended-release tablets are contained in a hard tablet shell that you may see in your bowel movement; this is normal.
- Dispose of expired, unwanted, or unused hydromorphone hydrochloride extended-release tablets by promptly flushing down the toilet, if a drug take-back option is not readily available. Visit www.fda.gov/drugdisposal for additional information on disposal of unused medicines.

While taking hydromorphone hydrochloride extended-release tablets, DO NOT:

- Drive or operate heavy machinery, until you know how hydromorphone hydrochloride extended-release tablets affect you. Hydromorphone hydrochloride extended-release tablets can make you sleepy, dizzy, or lightheaded.
- Drink alcohol or use prescription or over-the-counter medicines containing alcohol. Using products containing alcohol during treatment with hydromorphone hydrochloride extended-release tablets may cause you to overdose and die.

The possible side effects of hydromorphone hydrochloride extended-release tablets are:

- constipation, nausea, sleepiness, vomiting, tiredness, headache, dizziness, abdominal pain. Call your healthcare provider if you have any of these symptoms and they are severe.

Get emergency medical help or call 911 right away if you have:

- trouble breathing, shortness of breath, fast heartbeat, chest pain, swelling of your face, tongue, or throat, extreme drowsiness, light-headedness when changing positions, feeling faint, agitation, high body temperature, trouble walking, stiff muscles, or mental changes such as confusion.

These are not all the possible side effects of hydromorphone hydrochloride extended-release tablets. Call your doctor for medical advice about side effects. You may report side effects to Trigen Laboratories, LLC at 1-800-444-5164 or FDA at 1-800-FDA-1088 or www.fda.gov/medwatch. For more information go to dailymed.nlm.nih.gov

Manufactured for:

Trigen Laboratories, LLC

Alpharetta, GA 30005

1-800-444-5164

www.trigenlab.com

This Medication Guide has been approved by the U.S. Food and Drug Administration.

Revised: 12/2025 200253-08

PRINCIPAL DISPLAY PANEL - 8 mg bottle

NDC 13811-701-10
100 TABLETS

HYDROmorphone Hydrochloride Extended-release Tablets
Once Daily
CII
8 mg
Rx only
Each tablet contains:
Hydromorphone Hydrochloride USP. . . . . . . 8 mg
For opioid tolerant patients only
Dispense the accompanying Medication Guide to each patient

PRINCIPAL DISPLAY PANEL - 12 mg bottle

NDC 13811-702-10
100 TABLETS
HYDROmorphone Hydrochloride Extended-release Tablets
Once Daily
CII
12 mg
Rx only
Each tablet contains:
Hydromorphone Hydrochloride USP. . . . . . . 12 mg
For opioid tolerant patients only
Dispense the accompanying Medication Guide to each patient

PRINCIPAL DISPLAY PANEL - 16 mg bottle

NDC 13811-703-10
100 TABLETS
HYDROmorphone Hydrochloride Extended-release Tablets
Once Daily
CII
16 mg
Rx only
Each tablet contains:
Hydromorphone Hydrochloride USP. . . . . . . 16 mg
For opioid tolerant patients only
Dispense the accompanying Medication Guide to each patient

PRINCIPAL DISPLAY PANEL - 24 mg bottle

NDC 13811-720-10
100 TABLETS
HYDROmorphone Hydrochloride Extended-release Tablets
Once Daily
CII
24 mg
Rx only
Each tablet contains:
Hydromorphone Hydrochloride USP. . . . . . . 24 mg
For opioid tolerant patients only
Dispense the accompanying Medication Guide to each patient

PRINCIPAL DISPLAY PANEL - 32 mg bottle

NDC 13811-704-10
100 TABLETS
HYDROmorphone Hydrochloride Extended-release Tablets
Once Daily
CII
32 mg
Rx only
Each tablet contains:
Hydromorphone Hydrochloride USP. . . . . . . 32 mg
For opioid tolerant patients only
Dispense the accompanying Medication Guide to each patient